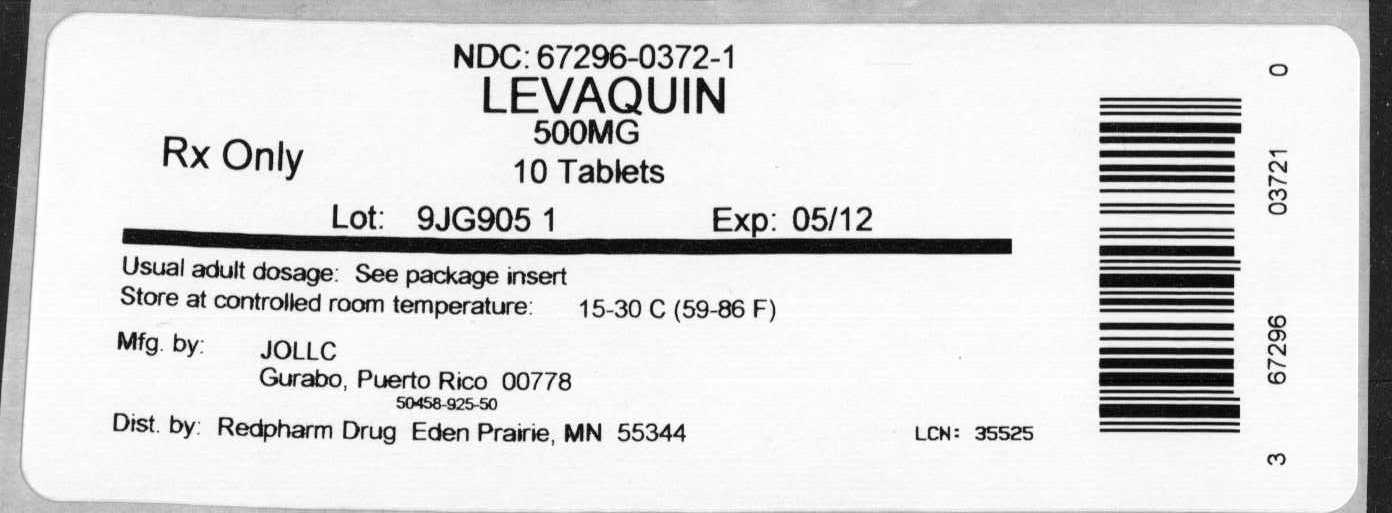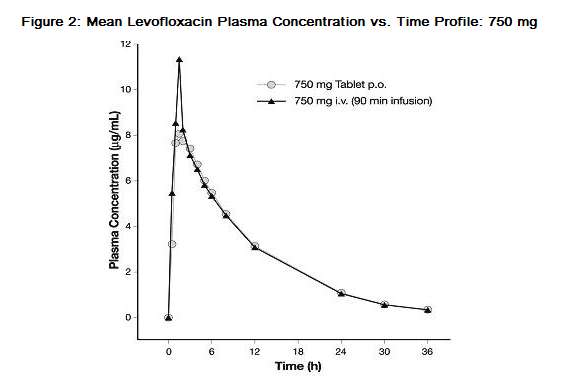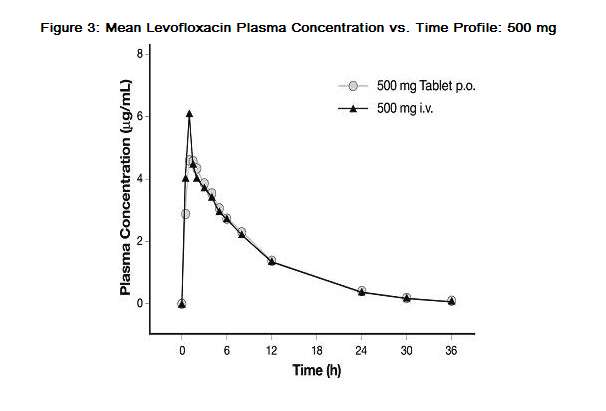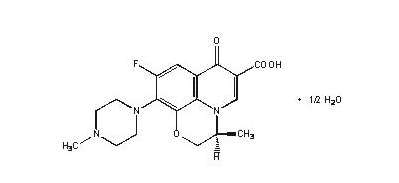 DRUG LABEL: LEVAQUIN
NDC: 67296-0372 | Form: TABLET, FILM COATED
Manufacturer: RedPharm Drug Inc.
Category: prescription | Type: HUMAN PRESCRIPTION DRUG LABEL
Date: 20110727

ACTIVE INGREDIENTS: levofloxacin 500 mg/1 1
INACTIVE INGREDIENTS: hypromelloses; crospovidone; cellulose, microcrystalline; magnesium stearate; polyethylene glycols; titanium dioxide; polysorbate 80; ferric oxide red; ferric oxide yellow

HIGHLIGHTS OF PRESCRIBING INFORMATION

These highlights do not include all the information needed to use LEVAQUIN® safely and effectively. See full prescribing information for LEVAQUIN.
LEVAQUIN® (levofloxacin) Tablet, Film Coated for Oral use
LEVAQUIN® (levofloxacin) Solution for Oral use
LEVAQUIN® (levofloxacin) Injection, Solution, Concentrate for Intravenous use
LEVAQUIN® (levofloxacin) Injection, Solution for Intravenous use
Initial U.S. Approval: 1996

WARNING:

Fluoroquinolones, including LEVAQUIN®, are associated with an increased risk of tendinitis and tendon rupture in all ages. This risk is further increased in older patients usually over 60 years of age, in patients taking corticosteroid drugs, and in patients with kidney, heart or lung transplants [See Warnings and Precautions (5.1)].

Fluoroquinolones, including LEVAQUIN®, may exacerbate muscle weakness in persons with myasthenia gravis. Avoid LEVAQUIN® in patients with a known history of myasthenia gravis [See Warnings and Precautions (5.2)].

MICROBIOLOGY

To reduce the development of drug-resistant bacteria and maintain the effectiveness of LEVAQUIN® and other antibacterial drugs, LEVAQUIN® should be used only to treat or prevent infections that are proven or strongly suspected to be caused by bacteria.

RECENT MAJOR CHANGES

Warnings and Precautions

- Exacerbation of myasthenia gravis (5.2) 01/2011

1 INDICATIONS AND USAGE

LEVAQUIN® is a fluoroquinolone antibacterial indicated in adults (≥18 years of age) with infections caused by designated, susceptible bacteria (1, 12.4).

- Pneumonia: nosocomial (1.1) and community acquired (1.2, 1.3)
- Acute bacterial sinusitis (1.4)
- Acute bacterial exacerbation of chronic bronchitis (1.5)
- Skin and skin structure infections: complicated (1.6) and uncomplicated (1.7)
- Chronic bacterial prostatitis (1.8)
- Urinary tract infections: complicated (1.9, 1.10) and uncomplicated (1.12)
- Acute pyelonephritis (1.11)
- Inhalational anthrax, post-exposure (1.13). Not tested in humans for post-exposure prevention of inhalational anthrax; plasma concentrations are likely to predict efficacy (14.9)

2 DOSAGE AND ADMINISTRATION

- Dosage in patients with normal renal function (2.1)

Type of Infection | Dose Every 24 hours | Duration (days)
Nosocomial Pneumonia (1.1) | 750 mg | 7–14
Community Acquired Pneumonia (1.2) | 500 mg | 7–14
Community Acquired Pneumonia (1.3) | 750 mg | 5
Acute Bacterial Sinusitis (1.4) | 750 mg | 5
 | 500 mg | 10–14
Acute Bacterial Exacerbation of Chronic Bronchitis (1.5) | 500 mg | 7
Complicated Skin and Skin Structure Infections (SSSI) (1.6) | 750 mg | 7–14
Uncomplicated SSSI (1.7) | 500 mg | 7–10
Chronic Bacterial Prostatitis (1.8) | 500 mg | 28
Complicated Urinary Tract Infection (1.9) or Acute Pyelonephritis (1.11) | 750 mg | 5
Complicated Urinary Tract Infection (1.10) or Acute Pyelonephritis (1.11) | 250 mg | 10
Uncomplicated Urinary Tract Infection (1.12) | 250 mg | 3
Inhalational Anthrax (Post-Exposure) (1.13)
Adults and Pediatric Patients > 50 kg and ≥ 6 months of age | 500 mg | 60
Pediatric Patients < 50 kg and ≥ 6 months of age | 8 mg/kg BID (not to exceed 250 mg/dose) | 60

- Adjust dose for creatinine clearance < 50 mL/min (2.3, 8.6, 12.3)
- IV Injection, Single-Use or Premix: Slow IV infusion only, over 60 or 90 minutes depending on dose. Avoid rapid or bolus IV (2.5)
- Dilute single-use vials to 5 mg/mL prior to IV infusion (2.6)
- Do not mix with other medications in vial or IV line (2.6)

3 DOSAGE FORMS AND STRENGTHS

Formulation (3) | Strength
Tablets | 250 mg, 500 mg, and 750 mg
Oral Solution | 25 mg/mL
Injection: single-use vials for dilution | 500 mg in 20 mL 750 mg in 30 mL
Injection: premix single-use flexible containers | 250 mg in 50 mL 500 mg in 100 mL 750 mg in 150 mL

4 CONTRAINDICATIONS

Known hypersensitivity to LEVAQUIN® or other quinolones (4, 5.3)

5 WARNINGS AND PRECAUTIONS

- Risk of tendinitis and tendon rupture is increased. This risk is further increased in older patients usually over 60 years of age, in patients taking corticosteroids, and in patients with kidney, heart or lung transplants. Discontinue if pain or inflammation in a tendon occurs (5.1, 8.5)
- May exacerbate muscle weakness in persons with myasthenia gravis. Avoid use in patients with a known history of myasthenia gravis (5.2).
- Anaphylactic reactions and allergic skin reactions, serious, occasionally fatal, may occur after first dose (4,5.3)
- Hematologic (including agranulocytosis, thrombocytopenia), and renal toxicities may occur after multiple doses (5.4)
- Hepatotoxicity: Severe, and sometimes fatal, hepatoxicity has been reported. Discontinue immediately if signs and symptoms of hepatitis occur (5.5)
- Central nervous system effects, including convulsions, anxiety, confusion, depression, and insomnia may occur after the first dose. Use with caution in patients with known or suspected disorders that may predispose them to seizures or lower the seizure threshold (5.6)
- Clostridium difficile-associated colitis: evaluate if diarrhea occurs (5.7)
- Peripheral neuropathy: discontinue if symptoms occur in order to prevent irreversibility (5.8)
- Prolongation of the QT interval and isolated cases of torsade de pointes have been reported. Avoid use in patients with known prolongation, those with hypokalemia, and with other drugs that prolong the QT interval (5.9, 8.5)

6 ADVERSE REACTIONS

The most common reactions (≥3%) were nausea, headache, diarrhea, insomnia, constipation and dizziness (6.2).

To report SUSPECTED ADVERSE REACTIONS, contact Ortho-McNeil-Janssen Scientific Affairs Customer Communications Center at 1-800-526-7736 or FDA at 1-800-FDA-1088 or www.fda.gov/medwatch.

7 DRUG INTERACTIONS

Interacting Drug | Interaction
Multivalent cation-containing products including antacids, metal cations or didanosine | Absorption of levofloxacin is decreased when the tablet or oral solution formulation is taken within 2 hours of these products. Do not co-administer the intravenous formulation in the same IV line with a multivalent cation, e.g., magnesium (2.4, 7.1)
Warfarin | Effect may be enhanced. Monitor prothrombin time, INR, watch for bleeding (7.2)
Antidiabetic agents | Carefully monitor blood glucose (5.11, 7.3)

8 USE IN SPECIFIC POPULATIONS

- Geriatrics: Severe hepatotoxicity has been reported. The majority of reports describe patients 65 years of age or older (5.5, 8.5, 17). May have increased risk of tendinopathy (including rupture), especially with concomitant corticosteroid use (5.1, 8.5, 17). May be more susceptible to prolongation of the QT interval. (5.9, 8.5, 17).
- Pediatrics: Musculoskeletal disorders (arthralgia, arthritis, tendinopathy, and gait abnormality) seen in more LEVAQUIN®-treated patients than in comparator. Shown to cause arthropathy and osteochondrosis in juvenile animals (5.10, 8.4, 13.2). Safety in pediatric patients treated for more than 14 days has not been studied. Risk-benefit appropriate only for the treatment of inhalational anthrax (post-exposure) (1.13, 2.2, 8.4, 14.9)

FULL PRESCRIBING INFORMATION

WARNING:

Fluoroquinolones, including LEVAQUIN®, are associated with an increased risk of tendinitis and tendon rupture in all ages. This risk is further increased in older patients usually over 60 years of age, in patients taking corticosteroid drugs, and in patients with kidney, heart or lung transplants [See Warnings and Precautions (5.1)].

Fluoroquinolones, including LEVAQUIN®, may exacerbate muscle weakness in persons with myasthenia gravis. Avoid LEVAQUIN® in patients with a known history of myasthenia gravis [See Warnings and Precautions (5.2)].

1 INDICATIONS AND USAGE

To reduce the development of drug-resistant bacteria and maintain the effectiveness of LEVAQUIN® and other antibacterial drugs, LEVAQUIN® should be used only to treat or prevent infections that are proven or strongly suspected to be caused by susceptible bacteria. When culture and susceptibility information are available, they should be considered in selecting or modifying antibacterial therapy. In the absence of such data, local epidemiology and susceptibility patterns may contribute to the empiric selection of therapy.

LEVAQUIN® Tablets/Injection and Oral Solution are indicated for the treatment of adults (≥18 years of age) with mild, moderate, and severe infections caused by susceptible strains of the designated microorganisms in the conditions listed in this section. LEVAQUIN® Injection is indicated when intravenous administration offers a route of administration advantageous to the patient (e.g., patient cannot tolerate an oral dosage form).

Culture and susceptibility testing

Appropriate culture and susceptibility tests should be performed before treatment in order to isolate and identify organisms causing the infection and to determine their susceptibility to levofloxacin [see Clinical Pharmacology (12.4)]. Therapy with LEVAQUIN® may be initiated before results of these tests are known; once results become available, appropriate therapy should be selected.

As with other drugs in this class, some strains of Pseudomonas aeruginosa may develop resistance fairly rapidly during treatment with LEVAQUIN®. Culture and susceptibility testing performed periodically during therapy will provide information about the continued susceptibility of the pathogens to the antimicrobial agent and also the possible emergence of bacterial resistance.

1.1 Nosocomial Pneumonia

LEVAQUIN® is indicated for the treatment of nosocomial pneumonia due to methicillin-susceptible Staphylococcus aureus, Pseudomonas aeruginosa, Serratia marcescens, Escherichia coli, Klebsiella pneumoniae, Haemophilus influenzae, or Streptococcus pneumoniae. Adjunctive therapy should be used as clinically indicated. Where Pseudomonas aeruginosa is a documented or presumptive pathogen, combination therapy with an anti-pseudomonal β-lactam is recommended [see Clinical Studies (14.1)].

1.2 Community-Acquired Pneumonia: 7–14 day Treatment Regimen

LEVAQUIN® is indicated for the treatment of community-acquired pneumonia due to methicillin-susceptible Staphylococcus aureus, Streptococcus pneumoniae (including multi-drug-resistant Streptococcus pneumoniae [MDRSP]), Haemophilus influenzae, Haemophilus parainfluenzae, Klebsiella pneumoniae, Moraxella catarrhalis, Chlamydophila pneumoniae, Legionella pneumophila, or Mycoplasma pneumoniae [see Dosage and Administration (2.1) and Clinical Studies (14.2)].

MDRSP isolates are strains resistant to two or more of the following antibacterials: penicillin (MIC ≥2 mcg/mL), 2nd generation cephalosporins, e.g., cefuroxime, macrolides, tetracyclines and trimethoprim/sulfamethoxazole.

1.3 Community-Acquired Pneumonia: 5-day Treatment Regimen

LEVAQUIN® is indicated for the treatment of community-acquired pneumonia due to Streptococcus pneumoniae (excluding multi-drug-resistant strains [MDRSP]), Haemophilus influenzae, Haemophilus parainfluenzae, Mycoplasma pneumoniae, or Chlamydophila pneumoniae [see Dosage and Administration (2.1) and Clinical Studies (14.3)].

1.4 Acute Bacterial Sinusitis: 5-day and 10–14 day Treatment Regimens

LEVAQUIN® is indicated for the treatment of acute bacterial sinusitis due to Streptococcus pneumoniae, Haemophilus influenzae, or Moraxella catarrhalis [see Clinical Studies (14.4)].

1.5 Acute Bacterial Exacerbation of Chronic Bronchitis

LEVAQUIN® is indicated for the treatment of acute bacterial exacerbation of chronic bronchitis due to methicillin-susceptible Staphylococcus aureus, Streptococcus pneumoniae, Haemophilus influenzae, Haemophilus parainfluenzae, or Moraxella catarrhalis.

1.6 Complicated Skin and Skin Structure Infections

LEVAQUIN® is indicated for the treatment of complicated skin and skin structure infections due to methicillin-susceptible Staphylococcus aureus, Enterococcus faecalis, Streptococcus pyogenes, or Proteus mirabilis [see Clinical Studies (14.5)].

1.7 Uncomplicated Skin and Skin Structure Infections

LEVAQUIN® is indicated for the treatment of uncomplicated skin and skin structure infections (mild to moderate) including abscesses, cellulitis, furuncles, impetigo, pyoderma, wound infections, due to methicillin-susceptible Staphylococcus aureus, or Streptococcus pyogenes.

1.8 Chronic Bacterial Prostatitis

LEVAQUIN® is indicated for the treatment of chronic bacterial prostatitis due to Escherichia coli, Enterococcus faecalis, or methicillin-susceptible Staphylococcus epidermidis [see Clinical Studies (14.6)].

1.9 Complicated Urinary Tract Infections: 5-day Treatment Regimen

LEVAQUIN® is indicated for the treatment of complicated urinary tract infections due to Escherichia coli, Klebsiella pneumoniae, or Proteus mirabilis [see Clinical Studies (14.7)].

1.10 Complicated Urinary Tract Infections: 10-day Treatment Regimen

LEVAQUIN® is indicated for the treatment of complicated urinary tract infections (mild to moderate) due to Enterococcus faecalis, Enterobacter cloacae, Escherichia coli, Klebsiella pneumoniae, Proteus mirabilis, or Pseudomonas aeruginosa [see Clinical Studies (14.8)].

1.11 Acute Pyelonephritis: 5 or 10-day Treatment Regimen

LEVAQUIN® is indicated for the treatment of acute pyelonephritis caused by Escherichia coli, including cases with concurrent bacteremia [see Clinical Studies (14.7, 14.8)].

1.12 Uncomplicated Urinary Tract Infections

LEVAQUIN® is indicated for the treatment of uncomplicated urinary tract infections (mild to moderate) due to Escherichia coli, Klebsiella pneumoniae, or Staphylococcus saprophyticus.

1.13 Inhalational Anthrax (Post-Exposure)

LEVAQUIN® is indicated for inhalational anthrax (post-exposure) to reduce the incidence or progression of disease following exposure to aerosolized Bacillus anthracis. The effectiveness of LEVAQUIN® is based on plasma concentrations achieved in humans, a surrogate endpoint reasonably likely to predict clinical benefit. LEVAQUIN® has not been tested in humans for the post-exposure prevention of inhalation anthrax. The safety of LEVAQUIN® in adults for durations of therapy beyond 28 days or in pediatric patients for durations of therapy beyond 14 days has not been studied. Prolonged LEVAQUIN® therapy should only be used when the benefit outweighs the risk [see Dosage and Administration (2.1, 2.2) and Clinical Studies (14.9)].

2 DOSAGE AND ADMINISTRATION

2.1 Dosage in Adult Patients with Normal Renal Function

The usual dose of LEVAQUIN® Tablets or Oral Solution is 250 mg, 500 mg, or 750 mg administered orally every 24 hours, as indicated by infection and described in Table 1. The usual dose of LEVAQUIN® Injection is 250 mg or 500 mg administered by slow infusion over 60 minutes every 24 hours or 750 mg administered by slow infusion over 90 minutes every 24 hours, as indicated by infection and described in Table 1.

These recommendations apply to patients with creatinine clearance ≥ 50 mL/min. For patients with creatinine clearance <50 mL/min, adjustments to the dosing regimen are required [see Dosage and Administration (2.3)].

Table 1: Dosage in Adult Patients with Normal Renal Function (creatinine clearance ≥ 50 mL/min)
Type of Infection [Due to the designated pathogens [see Indications and Usage (1)].] | Dosed Every 24 hours | Duration (days) [Sequential therapy (intravenous to oral) may be instituted at the discretion of the physician.]
Nosocomial Pneumonia | 750 mg | 7–14
Community Acquired Pneumonia [Due to methicillin-susceptible Staphylococcus aureus, Streptococcus pneumoniae (including multi-drug-resistant strains [MDRSP]), Haemophilus influenzae, Haemophilus parainfluenzae, Klebsiella pneumoniae, Moraxella catarrhalis, Chlamydophila pneumoniae, Legionella pneumophila, or Mycoplasma pneumoniae [see Indications and Usage (1.2)].] | 500 mg | 7–14
Community Acquired Pneumonia [Due to Streptococcus pneumoniae (excluding multi-drug-resistant strains [MDRSP]), Haemophilus influenzae, Haemophilus parainfluenzae, Mycoplasma pneumoniae, or Chlamydophila pneumoniae [see Indications and Usage (1.3)].] | 750 mg | 5
Acute Bacterial Sinusitis | 750 mg | 5
Acute Bacterial Sinusitis | 500 mg | 10–14
Acute Bacterial Exacerbation of Chronic Bronchitis | 500 mg | 7
Complicated Skin and Skin Structure Infections (SSSI) | 750 mg | 7–14
Uncomplicated SSSI | 500 mg | 7–10
Chronic Bacterial Prostatitis | 500 mg | 28
Complicated Urinary Tract Infection (cUTI) or Acute Pyelonephritis (AP) [This regimen is indicated for cUTI due to Escherichia coli, Klebsiella pneumoniae, Proteus mirabilis and AP due to E. coli, including cases with concurrent bacteremia.] | 750 mg | 5
Complicated Urinary Tract Infection (cUTI) or Acute Pyelonephritis (AP) [This regimen is indicated for cUTI due to Enterococcus faecalis, Enterococcus cloacae, Escherichia coli, Klebsiella pneumoniae, Proteus mirabilis, Pseudomonas aeruginosa; and for AP due to E. coli.] | 250 mg | 10
Uncomplicated Urinary Tract Infection | 250 mg | 3
Inhalational Anthrax (Post-Exposure), adult and pediatric patients > 50 kg and ≥ 6 months of age [Drug administration should begin as soon as possible after suspected or confirmed exposure to aerosolized B. anthracis. This indication is based on a surrogate endpoint. Levofloxacin plasma concentrations achieved in humans are reasonably likely to predict clinical benefit [see Clinical Studies (14.9)].] , [The safety of LEVAQUIN® in adults for durations of therapy beyond 28 days or in pediatric patients for durations beyond 14 days has not been studied. An increased incidence of musculoskeletal adverse events compared to controls has been observed in pediatric patients [see Warnings and Precautions (5.10), Use in Specific Populations (8.4), and Clinical Studies (14.9)]. Prolonged LEVAQUIN® therapy should only be used when the benefit outweighs the risk.] | 500 mg | 60
Pediatric patients < 50 kg and ≥ 6 months of age, | see Table 2 below (2.2) | 60

2.2 Dosage in Pediatric Patients

The dosage in pediatric patients ≥ 6 months of age is described below in Table 2.

Table 2: Dosage in Pediatric Patients ≥ 6 months of age
Type of Infection [Due to Bacillus anthracis [see Indications and Usage (1.13)]] | Dose | Freq. Once every | Duration [Sequential therapy (intravenous to oral) may be instituted at the discretion of the physician.]
Inhalational Anthrax (post-exposure) [Drug administration should begin as soon as possible after suspected or confirmed exposure to aerosolized B. anthracis. This indication is based on a surrogate endpoint. Levofloxacin plasma concentrations achieved in humans are reasonably likely to predict clinical benefit [see Clinical Studies (14.9)]] , [The safety of LEVAQUIN® in pediatric patients for durations of therapy beyond 14 days has not been studied. An increased incidence of musculoskeletal adverse events compared to controls has been observed in pediatric patients [see Warnings and Precautions (5.10), Use in Specific Populations (8.4), and Clinical Studies (14.9)]. Prolonged LEVAQUIN® therapy should only be used when the benefit outweighs the risk.]
Pediatric patients > 50 kg and ≥ 6 months of age | 500 mg | 24 hr | 60 days
Pediatric patients < 50 kg and ≥ 6 months of age | 8 mg/kg (not to exceed 250 mg per dose) | 12 hr | 60 days

2.3 Dosage Adjustment in Adults with Renal Impairment

Administer LEVAQUIN® with caution in the presence of renal insufficiency. Careful clinical observation and appropriate laboratory studies should be performed prior to and during therapy since elimination of levofloxacin may be reduced.

No adjustment is necessary for patients with a creatinine clearance ≥ 50 mL/min.

In patients with impaired renal function (creatinine clearance <50 mL/min), adjustment of the dosage regimen is necessary to avoid the accumulation of levofloxacin due to decreased clearance [see Use in Specific Populations (8.6)].

Table 3 shows how to adjust dose based on creatinine clearance.

Table 3: Dosage Adjustment in Adult Patients with Renal Impairment (creatinine clearance <50 mL/min)
Dosage in Normal Renal Function Every 24 hours | Creatinine Clearance 20 to 49 mL/min | Creatinine Clearance 10 to 19 mL/min | Hemodialysis or Chronic Ambulatory Peritoneal Dialysis (CAPD)
750 mg | 750 mg every 48 hours | 750 mg initial dose, then 500 mg every 48 hours | 750 mg initial dose, then 500 mg every 48 hours
500 mg | 500 mg initial dose, then 250 mg every 24 hours | 500 mg initial dose, then 250 mg every 48 hours | 500 mg initial dose, then 250 mg every 48 hours
250 mg | No dosage adjustment required | 250 mg every 48 hours. If treating uncomplicated UTI, then no dosage adjustment is required | No information on dosing adjustment is available

2.4 Drug Interaction With Chelation Agents: Antacids, Sucralfate, Metal Cations, Multivitamins

LEVAQUIN® Tablets and Oral Solution

LEVAQUIN® Tablets and Oral Solution should be administered at least two hours before or two hours after antacids containing magnesium, aluminum, as well as sucralfate, metal cations such as iron, and multivitamin preparations with zinc or didanosine chewable/buffered tablets or the pediatric powder for oral solution [see Drug Interactions (7.1) and Patient Counseling Information (17.2)].

LEVAQUIN® Injection

LEVAQUIN® Injection should not be co-administered with any solution containing multivalent cations, e.g., magnesium, through the same intravenous line [see Dosage and Administration (2.6)].

2.5 Administration Instructions

Food and LEVAQUIN® Tablets and Oral Solution

LEVAQUIN® Tablets can be administered without regard to food. It is recommended that LEVAQUIN® Oral Solution be taken 1 hour before or 2 hours after eating.

LEVAQUIN® Injection

Caution: Rapid or bolus intravenous infusion of LEVAQUIN® has been associated with hypotension and must be avoided. LEVAQUIN® Injection should be infused intravenously slowly over a period of not less than 60 or 90 minutes, depending on the dosage. LEVAQUIN® Injection should be administered only by intravenous infusion. It is not for intramuscular, intrathecal, intraperitoneal, or subcutaneous administration.

Hydration for Patients Receiving LEVAQUIN® Tablets, Oral Solution, and Injection

Adequate hydration of patients receiving oral or intravenous LEVAQUIN® should be maintained to prevent the formation of highly concentrated urine. Crystalluria and cylindruria have been reported with quinolones [see Adverse Reactions (6.1) and Patient Counseling Information (17.2)].

2.6 Preparation of Intravenous Product

Parenteral drug products should be inspected visually for particulate matter and discoloration prior to administration, whenever solution and container permit.

Because only limited data are available on the compatibility of LEVAQUIN® Injection with other intravenous substances, additives or other medications should not be added to LEVAQUIN® Injection Premix in Single-Use Flexible Containers and LEVAQUIN® Injection in Single-Use Vials, or infused simultaneously through the same intravenous line. If the same intravenous line is used for sequential infusion of several different drugs, the line should be flushed before and after infusion of LEVAQUIN® Injection with an infusion solution compatible with LEVAQUIN® Injection and with any other drug(s) administered via this common line.

LEVAQUIN® Injection in Single-Use Vials

Single-use vials require dilution prior to administration.

LEVAQUIN® Injection is supplied in single-use vials containing a concentrated levofloxacin solution with the equivalent of 500 mg (20 mL vial) and 750 mg (30 mL vial) of levofloxacin in Water for Injection, USP. The 20 mL and 30 mL vials each contain 25 mg of levofloxacin/mL. These LEVAQUIN® Injection single-use vials must be further diluted with an appropriate solution prior to intravenous administration [see Table 4]. The concentration of the resulting diluted solution should be 5 mg/mL prior to administration.

Compatible Intravenous Solutions: Any of the following intravenous solutions may be used to prepare a 5 mg/mL levofloxacin solution with the approximate pH values:

Table 4: Compatible Intravenous Solutions
Intravenous Fluids | Final pH of LEVAQUIN® Solution
0.9% Sodium Chloride Injection, USP | 4.71
5% Dextrose Injection, USP | 4.58
5% Dextrose/0.9% NaCl Injection | 4.62
5% Dextrose in Lactated Ringers | 4.92
Plasma-Lyte® 56/5% Dextrose Injection | 5.03
5% Dextrose, 0.45% Sodium Chloride, and 0.15% Potassium Chloride Injection | 4.61
Sodium Lactate Injection (M/6) | 5.54

Since no preservative or bacteriostatic agent is present in this product, aseptic technique must be used in preparation of the final intravenous solution. Since the vials are for single-use only, any unused portion remaining in the vial should be discarded. When used to prepare two 250 mg doses from the 20 mL vial containing 500 mg of levofloxacin, the full content of the vial should be withdrawn at once using a single-entry procedure, and a second dose should be prepared and stored for subsequent use [see Stability of LEVAQUIN® Injection Following Dilution].

Prepare the desired dosage of levofloxacin according to Table 5:

Table 5: Preparation of LEVAQUIN® Intravenous Solution
Desired Dosage Strength | From Appropriate Vial, Withdraw Volume | Volume of Diluent | Infusion Time
250 mg | 10 mL (20 mL Vial) | 40 mL | 60 min
500 mg | 20 mL (20 mL Vial) | 80 mL | 60 min
750 mg | 30 mL (30 mL Vial) | 120 mL | 90 min

For example, to prepare a 500 mg dose using the 20 mL vial (25 mg/mL), withdraw 20 mL and dilute with a compatible intravenous solution to a total volume of 100 mL.

This intravenous drug product should be inspected visually for particulate matter prior to administration. Samples containing visible particles should be discarded.

Stability of LEVAQUIN® Injection Following Dilution: LEVAQUIN® Injection, when diluted in a compatible intravenous fluid to a concentration of 5 mg/mL, is stable for 72 hours when stored at or below 25°C (77°F) and for 14 days when stored under refrigeration at 5°C (41°F) in plastic intravenous containers. Solutions that are diluted in a compatible intravenous solution and frozen in glass bottles or plastic intravenous containers are stable for 6 months when stored at - 20°C (- 4°F). Thaw frozen solutions at room temperature 25°C (77°F) or in a refrigerator 8°C (46°F). Do not force thaw by microwave irradiation or water bath immersion. Do not refreeze after initial thawing.

LEVAQUIN® Injection Premix in Single-Use Flexible Containers (5 mg/mL)

LEVAQUIN® Injection is also supplied in flexible containers within a foil overwrap. These contain a premixed, ready to use levofloxacin solution in 5% dextrose (D5W) for single-use. The 100 mL premixed flexible containers contain either 250 mg/50 mL or 500 mg/100 mL of levofloxacin solution. The 150 mL flexible container contains 750 mg/150 mL of levofloxacin solution. The concentration of each container is 5 mg/mL. No further dilution of these preparations is necessary. Because the premix flexible containers are for single-use only, any unused portion should be discarded.

Instructions for the Use of LEVAQUIN® Injection Premix in Flexible Containers:

1. Tear outer wrap at the notch and remove solution container.
2. Check the container for minute leaks by squeezing the inner bag firmly. If leaks are found, or if the seal is not intact, discard the solution, as the sterility may be compromised.
3. Do not use if the solution is cloudy or a precipitate is present.
4. Use sterile equipment.
5. WARNING: Do not use flexible containers in series connections. Such use could result in air embolism due to residual air being drawn from the primary container before administration of the fluid from the secondary container is complete.

Preparation for Administration:

1. Close flow control clamp of administration set.
2. Remove cover from port at bottom of container.
3. Insert piercing pin of administration set into port with a twisting motion until the pin is firmly seated. NOTE: See full directions on administration set carton.
4. Suspend container from hanger.
5. Squeeze and release drip chamber to establish proper fluid level in chamber during infusion of LEVAQUIN® Injection Premix in Flexible Containers.
6. Open flow control clamp to expel air from set. Close clamp.
7. Regulate rate of administration with flow control clamp.

3 DOSAGE FORMS AND STRENGTHS

TABLETS, Film-coated, capsule-shaped

- 250 mg terra cotta pink tablets, imprinted with "250" on one side and "LEVAQUIN" on the other
- 500 mg peach tablets, imprinted with "500" on one side and "LEVAQUIN" on the other
- 750 mg white tablets, imprinted with "750" on one side and "LEVAQUIN" on the other

ORAL SOLUTION, 25mg/mL, clear yellow to clear greenish-yellow color

INJECTION, Single-Use Vials of concentrated solution for dilution for intravenous infusion, clear yellow to clear greenish-yellow in appearance

- 20 mL vial of 25 mg/mL levofloxacin solution, equivalent to 500 mg of levofloxacin
- 30 mL vial of 25 mg/mL levofloxacin solution, equivalent to 750 mg of levofloxacin

INJECTION (5 mg/mL in 5% Dextrose) Premix in Single-Use Flexible Containers, for intravenous infusion

- 100 mL container, fill volume 50 mL (equivalent to 250 mg levofloxacin)
- 100 mL container, fill volume 100 mL (equivalent to 500 mg levofloxacin)
- 150 mL container, fill volume 150 mL (equivalent to 750 mg levofloxacin)

4 CONTRAINDICATIONS

LEVAQUIN® is contraindicated in persons with known hypersensitivity to levofloxacin, or other quinolone antibacterials [see Warnings and Precautions (5.3)].

5 WARNINGS AND PRECAUTIONS

5.1 Tendinopathy and Tendon Rupture

Fluoroquinolones, including LEVAQUIN®, are associated with an increased risk of tendinitis and tendon rupture in all ages. This adverse reaction most frequently involves the Achilles tendon, and rupture of the Achilles tendon may require surgical repair. Tendinitis and tendon rupture in the rotator cuff (the shoulder), the hand, the biceps, the thumb, and other tendon sites have also been reported. The risk of developing fluoroquinolone-associated tendinitis and tendon rupture is further increased in older patients usually over 60 years of age, in those taking corticosteroid drugs, and in patients with kidney, heart or lung transplants. Factors, in addition to age and corticosteroid use, that may independently increase the risk of tendon rupture include strenuous physical activity, renal failure, and previous tendon disorders such as rheumatoid arthritis. Tendinitis and tendon rupture have been reported in patients taking fluoroquinolones who do not have the above risk factors. Tendon rupture can occur during or after completion of therapy; cases occurring up to several months after completion of therapy have been reported. LEVAQUIN® should be discontinued if the patient experiences pain, swelling, inflammation or rupture of a tendon. Patients should be advised to rest at the first sign of tendinitis or tendon rupture, and to contact their healthcare provider regarding changing to a non-quinolone antimicrobial drug. [see Adverse Reactions (6.3); Patient Counseling Information (17.3)].

5.2 Exacerbation of Myasthenia Gravis

Fluoroquinolones, including LEVAQUIN®, have neuromuscular blocking activity and may exacerbate muscle weakness in persons with myasthenia gravis. Postmarketing serious adverse events, including deaths and requirement for ventilatory support, have been associated with fluoroquinolone use in persons with myasthenia gravis. Avoid LEVAQUIN® in patients with a known history of myasthenia gravis [see Adverse Reactions (6.3); Patient Counseling Information (17.3)].

5.3 Hypersensitivity Reactions

Serious and occasionally fatal hypersensitivity and/or anaphylactic reactions have been reported in patients receiving therapy with fluoroquinolones, including LEVAQUIN®. These reactions often occur following the first dose. Some reactions have been accompanied by cardiovascular collapse, hypotension/shock, seizure, loss of consciousness, tingling, angioedema (including tongue, laryngeal, throat, or facial edema/swelling), airway obstruction (including bronchospasm, shortness of breath, and acute respiratory distress), dyspnea, urticaria, itching, and other serious skin reactions. LEVAQUIN® should be discontinued immediately at the first appearance of a skin rash or any other sign of hypersensitivity. Serious acute hypersensitivity reactions may require treatment with epinephrine and other resuscitative measures, including oxygen, intravenous fluids, antihistamines, corticosteroids, pressor amines, and airway management, as clinically indicated [see Adverse Reactions (6); Patient Counseling Information (17.3)].

5.4 Other Serious and Sometimes Fatal Reactions

Other serious and sometimes fatal events, some due to hypersensitivity, and some due to uncertain etiology, have been reported rarely in patients receiving therapy with fluoroquinolones, including LEVAQUIN®. These events may be severe and generally occur following the administration of multiple doses. Clinical manifestations may include one or more of the following:

- fever, rash, or severe dermatologic reactions (e.g., toxic epidermal necrolysis, Stevens-Johnson Syndrome);
- vasculitis; arthralgia; myalgia; serum sickness;
- allergic pneumonitis;
- interstitial nephritis; acute renal insufficiency or failure;
- hepatitis; jaundice; acute hepatic necrosis or failure;
- anemia, including hemolytic and aplastic; thrombocytopenia, including thrombotic thrombocytopenic purpura; leukopenia; agranulocytosis; pancytopenia; and/or other hematologic abnormalities.

The drug should be discontinued immediately at the first appearance of skin rash, jaundice, or any other sign of hypersensitivity and supportive measures instituted [see Adverse Reactions (6); Patient Counseling Information (17.3)].

5.5 Hepatotoxicity

Post-marketing reports of severe hepatotoxicity (including acute hepatitis and fatal events) have been received for patients treated with LEVAQUIN®. No evidence of serious drug-associated hepatotoxicity was detected in clinical trials of over 7,000 patients. Severe hepatotoxicity generally occurred within 14 days of initiation of therapy and most cases occurred within 6 days. Most cases of severe hepatotoxicity were not associated with hypersensitivity [see Warnings and Precautions (5.4)]. The majority of fatal hepatotoxicity reports occurred in patients 65 years of age or older and most were not associated with hypersensitivity. LEVAQUIN® should be discontinued immediately if the patient develops signs and symptoms of hepatitis [see Adverse Reactions (6); Patient Counseling Information (17.3)].

5.6 Central Nervous System Effects

Convulsions and toxic psychoses have been reported in patients receiving fluoroquinolones, including LEVAQUIN®. Fluoroquinolones may also cause increased intracranial pressure and central nervous system stimulation which may lead to tremors, restlessness, anxiety, lightheadedness, confusion, hallucinations, paranoia, depression, nightmares, insomnia, and, rarely, suicidal thoughts or acts. These reactions may occur following the first dose. If these reactions occur in patients receiving LEVAQUIN®, the drug should be discontinued and appropriate measures instituted. As with other fluoroquinolones, LEVAQUIN® should be used with caution in patients with a known or suspected central nervous system (CNS) disorder that may predispose them to seizures or lower the seizure threshold (e.g., severe cerebral arteriosclerosis, epilepsy) or in the presence of other risk factors that may predispose them to seizures or lower the seizure threshold (e.g., certain drug therapy, renal dysfunction.) [see Adverse Reactions (6); Drug Interactions (7.4, 7.5); Patient Counseling Information (17.3)].

5.7 Clostridium difficile-Associated Diarrhea

Clostridium difficile-associated diarrhea (CDAD) has been reported with use of nearly all antibacterial agents, including LEVAQUIN®, and may range in severity from mild diarrhea to fatal colitis. Treatment with antibacterial agents alters the normal flora of the colon leading to overgrowth of C. difficile.

C. difficile produces toxins A and B which contribute to the development of CDAD. Hypertoxin producing strains of C. difficile cause increased morbidity and mortality, as these infections can be refractory to antimicrobial therapy and may require colectomy. CDAD must be considered in all patients who present with diarrhea following antibiotic use. Careful medical history is necessary since CDAD has been reported to occur over two months after the administration of antibacterial agents.

If CDAD is suspected or confirmed, ongoing antibiotic use not directed against C. difficile may need to be discontinued. Appropriate fluid and electrolyte management, protein supplementation, antibiotic treatment of C. difficile, and surgical evaluation should be instituted as clinically indicated [see Adverse Reactions (6.2), Patient Counseling Information (17.3)].

5.8 Peripheral Neuropathy

Rare cases of sensory or sensorimotor axonal polyneuropathy affecting small and/or large axons resulting in paresthesias, hypoesthesias, dysesthesias and weakness have been reported in patients receiving fluoroquinolones, including LEVAQUIN®. LEVAQUIN® should be discontinued if the patient experiences symptoms of neuropathy including pain, burning, tingling, numbness, and/or weakness or other alterations of sensation including light touch, pain, temperature, position sense, and vibratory sensation in order to prevent the development of an irreversible condition [see Adverse Reactions (6), Patient Counseling Information (17.3)].

5.9 Prolongation of the QT Interval

Some fluoroquinolones, including LEVAQUIN®, have been associated with prolongation of the QT interval on the electrocardiogram and infrequent cases of arrhythmia. Rare cases of torsade de pointes have been spontaneously reported during postmarketing surveillance in patients receiving fluoroquinolones, including LEVAQUIN®. LEVAQUIN® should be avoided in patients with known prolongation of the QT interval, patients with uncorrected hypokalemia, and patients receiving Class IA (quinidine, procainamide), or Class III (amiodarone, sotalol) antiarrhythmic agents. Elderly patients may be more susceptible to drug-associated effects on the QT interval [see Adverse Reactions (6.3), Use in Specific Populations (8.5), and Patient Counseling Information (17.3)].

5.10 Musculoskeletal Disorders in Pediatric Patients and Arthropathic Effects in Animals

LEVAQUIN® is indicated in pediatric patients (≥6 months of age) only for the prevention of inhalational anthrax (post-exposure) [see Indications and Usage (1.13)]. An increased incidence of musculoskeletal disorders (arthralgia, arthritis, tendinopathy, and gait abnormality) compared to controls has been observed in pediatric patients receiving LEVAQUIN® [see Use in Specific Populations (8.4)].

In immature rats and dogs, the oral and intravenous administration of levofloxacin resulted in increased osteochondrosis. Histopathological examination of the weight-bearing joints of immature dogs dosed with levofloxacin revealed persistent lesions of the cartilage. Other fluoroquinolones also produce similar erosions in the weight-bearing joints and other signs of arthropathy in immature animals of various species [see Animal Toxicology and/or Pharmacology (13.2)].

5.11 Blood Glucose Disturbances

As with other fluoroquinolones, disturbances of blood glucose, including symptomatic hyper- and hypoglycemia, have been reported with LEVAQUIN®, usually in diabetic patients receiving concomitant treatment with an oral hypoglycemic agent (e.g., glyburide) or with insulin. In these patients, careful monitoring of blood glucose is recommended. If a hypoglycemic reaction occurs in a patient being treated with LEVAQUIN®, LEVAQUIN® should be discontinued and appropriate therapy should be initiated immediately [see Adverse Reactions (6.2); Drug Interactions (7.3); Patient Counseling Information (17.4)].

5.12 Photosensitivity/Phototoxicity

Moderate to severe photosensitivity/phototoxicity reactions, the latter of which may manifest as exaggerated sunburn reactions (e.g., burning, erythema, exudation, vesicles, blistering, edema) involving areas exposed to light (typically the face, "V" area of the neck, extensor surfaces of the forearms, dorsa of the hands), can be associated with the use of fluoroquinolones after sun or UV light exposure. Therefore, excessive exposure to these sources of light should be avoided. Drug therapy should be discontinued if photosensitivity/phototoxicity occurs [see Adverse Reactions (6.3); Patient Counseling Information (17.3)].

5.13 Development of Drug Resistant Bacteria

Prescribing LEVAQUIN® in the absence of a proven or strongly suspected bacterial infection or a prophylactic indication is unlikely to provide benefit to the patient and increases the risk of the development of drug-resistant bacteria [see Patient Counseling Information (17.1)].

6 ADVERSE REACTIONS

6.1 Serious and Otherwise Important Adverse Reactions

The following serious and otherwise important adverse drug reactions are discussed in greater detail in other sections of labeling:

- Tendon Effects [see Warnings and Precautions (5.1)]
- Exacerbation of Myasthenia Gravis [see Warnings and Precautions (5.2)]
- Hypersensitivity Reactions [see Warnings and Precautions (5.3)]
- Other Serious and Sometimes Fatal Reactions [see Warnings and Precautions (5.4)]
- Hepatotoxicity [see Warnings and Precautions (5.5)]
- Central Nervous System Effects [see Warnings and Precautions (5.6)]
- Clostridium difficile-Associated Diarrhea [see Warnings and Precautions (5.7)]
- Peripheral Neuropathy [see Warnings and Precautions (5.8)]
- Prolongation of the QT Interval [see Warnings and Precautions (5.9)]
- Musculoskeletal Disorders in Pediatric Patients [see Warnings and Precautions (5.10)]
- Blood Glucose Disturbances [see Warnings and Precautions (5.11)]
- Photosensitivity/Phototoxicity [see Warnings and Precautions (5.12)]
- Development of Drug Resistant Bacteria [see Warnings and Precautions (5.13)]

Hypotension has been associated with rapid or bolus intravenous infusion of LEVAQUIN®. LEVAQUIN® should be infused slowly over 60 to 90 minutes, depending on dosage [see Dosage and Administration (2.5)].

Crystalluria and cylindruria have been reported with quinolones, including LEVAQUIN®. Therefore, adequate hydration of patients receiving LEVAQUIN® should be maintained to prevent the formation of a highly concentrated urine [see Dosage and Administration (2.5)].

6.2 Clinical Trial Experience

Because clinical trials are conducted under widely varying conditions, adverse reaction rates observed in the clinical trials of a drug cannot be directly compared to rates in the clinical trials of another drug and may not reflect the rates observed in practice.

The data described below reflect exposure to LEVAQUIN® in 7537 patients in 29 pooled Phase 3 clinical trials. The population studied had a mean age of 50 years (approximately 74% of the population was < 65 years of age), 50% were male, 71% were Caucasian, 19% were Black. Patients were treated with LEVAQUIN® for a wide variety of infectious diseases [see Indications and Usage (1)]. Patients received LEVAQUIN® doses of 750 mg once daily, 250 mg once daily, or 500 mg once or twice daily. Treatment duration was usually 3–14 days, and the mean number of days on therapy was 10 days.

The overall incidence, type and distribution of adverse reactions was similar in patients receiving LEVAQUIN® doses of 750 mg once daily, 250 mg once daily, and 500 mg once or twice daily. Discontinuation of LEVAQUIN® due to adverse drug reactions occurred in 4.3% of patients overall, 3.8% of patients treated with the 250 mg and 500 mg doses and 5.4% of patients treated with the 750 mg dose. The most common adverse drug reactions leading to discontinuation with the 250 and 500 mg doses were gastrointestinal (1.4%), primarily nausea (0.6%); vomiting (0.4%); dizziness (0.3%); and headache (0.2%). The most common adverse drug reactions leading to discontinuation with the 750 mg dose were gastrointestinal (1.2%), primarily nausea (0.6%), vomiting (0.5%); dizziness (0.3%); and headache (0.3%).

Adverse reactions occurring in ≥1% of LEVAQUIN®-treated patients and less common adverse reactions, occurring in 0.1 to <1% of LEVAQUIN®-treated patients, are shown in Table 6 and Table 7, respectively. The most common adverse drug reactions (≥3%) are nausea, headache, diarrhea, insomnia, constipation, and dizziness.

Table 6: Common (≥1%) Adverse Reactions Reported in Clinical Trials with LEVAQUIN®
System/Organ Class | Adverse Reaction | % (N=7537)
Infections and Infestations | moniliasis | 1
Psychiatric Disorders | insomnia [N=7274] [see Warnings and Precautions (5.6)] | 4
Nervous System Disorders | headache dizziness [see Warnings and Precautions (5.6)] | 6 3
Respiratory, Thoracic and Mediastinal Disorders | dyspnea [see Warnings and Precautions (5.3)] | 1
Gastrointestinal Disorders | nausea | 7
Gastrointestinal Disorders | diarrhea | 5
Gastrointestinal Disorders | constipation | 3
Gastrointestinal Disorders | abdominal pain | 2
Gastrointestinal Disorders | vomiting | 2
Gastrointestinal Disorders | dyspepsia | 2
Skin and Subcutaneous Tissue Disorders | rash [see Warnings and Precautions (5.3)] pruritus | 2 1
Reproductive System and Breast Disorders | vaginitis | 1 [N=3758 (women)]
General Disorders and Administration Site Conditions | edema | 1
General Disorders and Administration Site Conditions | injection site reaction | 1
General Disorders and Administration Site Conditions | chest pain | 1

Table 7: Less Common (0.1 to 1%) Adverse Reactions Reported in Clinical Trials with LEVAQUIN® (N=7537)
System/Organ Class | Adverse Reaction
Infections and Infestations | genital moniliasis
Blood and Lymphatic System Disorders | anemia thrombocytopenia granulocytopenia [see Warnings and Precautions (5.4)]
Immune System Disorders | allergic reaction [see Warnings and Precautions (5.3,5.4)]
Metabolism and Nutrition Disorders | hyperglycemia hypoglycemia [see Warnings and Precautions (5.11)] hyperkalemia
Psychiatric Disorders | anxiety agitation confusion depression hallucination nightmare [N = 7274] [see Warnings and Precautions (5.6)] sleep disorder anorexia abnormal dreaming
Nervous System Disorders | tremor convulsions [see Warnings and Precautions (5.6)] paresthesia [see Warnings and Precautions (5.8)] vertigo hypertonia hyperkinesias abnormal gait somnolence syncope
Respiratory, Thoracic and Mediastinal Disorders | epistaxis
Cardiac Disorders | cardiac arrest palpitation ventricular tachycardia ventricular arrhythmia
Vascular Disorders | phlebitis
Gastrointestinal Disorders | gastritis stomatitis pancreatitis esophagitis gastroenteritis glossitis pseudomembraneous/ C. difficile colitis [see Warnings and Precautions (5.7)]
Hepatobiliary Disorders | abnormal hepatic function increased hepatic enzymes increased alkaline phosphatase
Skin and Subcutaneous Tissue Disorders | urticaria [see Warnings and Precautions (5.3)]
Musculoskeletal and Connective Tissue Disorders | arthralgia tendinitis [see Warnings and Precautions (5.1)] myalgia skeletal pain
Renal and Urinary Disorders | abnormal renal function acute renal failure [see Warnings and Precautions (5.4)]

In clinical trials using multiple-dose therapy, ophthalmologic abnormalities, including cataracts and multiple punctate lenticular opacities, have been noted in patients undergoing treatment with quinolones, including LEVAQUIN®. The relationship of the drugs to these events is not presently established.

6.3 Postmarketing Experience

Table 8 lists adverse reactions that have been identified during post-approval use of LEVAQUIN®. Because these reactions are reported voluntarily from a population of uncertain size, reliably estimating their frequency or establishing a causal relationship to drug exposure is not always possible.

Table 8: Postmarketing Reports Of Adverse Drug Reactions
System/Organ Class | Adverse Reaction
Blood and Lymphatic System Disorders | pancytopenia aplastic anemia leukopenia hemolytic anemia [see Warnings and Precautions (5.4)] eosinophilia
Immune System Disorders | hypersensitivity reactions, sometimes fatal including: anaphylactic/anaphylactoid reactions anaphylactic shock angioneurotic edema serum sickness [see Warnings and Precautions (5.3,5.4)]
Psychiatric Disorders | psychosis paranoia isolated reports of suicide attempt and suicidal ideation [see Warnings and Precautions (5.6)]
Nervous System Disorders | exacerbation of myasthenia gravis [see Warnings and Precautions (5.2)] anosmia ageusia parosmia dysgeusia peripheral neuropathy [see Warnings and Precautions (5.8)] isolated reports of encephalopathy abnormal electroencephalogram (EEG) dysphonia
Eye Disorders | vision disturbance, including diplopia visual acuity reduced vision blurred scotoma
Ear and Labyrinth Disorders | hypoacusis tinnitus
Cardiac Disorders | isolated reports of torsade de pointes electrocardiogram QT prolonged [see Warnings and Precautions (5.9)] tachycardia
Vascular Disorders | vasodilatation
Respiratory, Thoracic and Mediastinal Disorders | isolated reports of allergic pneumonitis [see Warnings and Precautions (5.4)]
Hepatobiliary Disorders | hepatic failure (including fatal cases) hepatitis jaundice [see Warnings and Precautions (5.4),(5.5)]
Skin and Subcutaneous Tissue Disorders | bullous eruptions to include: Stevens-Johnson Syndrome toxic epidermal necrolysis erythema multiforme [see Warnings and Precautions (5.4)] photosensitivity/phototoxicity reaction [see Warnings and Precautions (5.12)] leukocytoclastic vasculitis
Musculoskeletal and Connective Tissue Disorders | tendon rupture [see Warnings and Precautions (5.1)] muscle injury, including rupture rhabdomyolysis
Renal and Urinary Disorders | interstitial nephritis [see Warnings and Precautions (5.4)]
General Disorders and Administration Site Conditions | multi-organ failure pyrexia
Investigations | prothrombin time prolonged international normalized ratio prolonged muscle enzymes increased

7 DRUG INTERACTIONS

7.1 Chelation Agents: Antacids, Sucralfate, Metal Cations, Multivitamins

LEVAQUIN® Tablets and Oral Solution

While the chelation by divalent cations is less marked than with other fluoroquinolones, concurrent administration of LEVAQUIN® Tablets and Oral Solution with antacids containing magnesium, or aluminum, as well as sucralfate, metal cations such as iron, and multivitamin preparations with zinc may interfere with the gastrointestinal absorption of levofloxacin, resulting in systemic levels considerably lower than desired. Tablets with antacids containing magnesium, aluminum, as well as sucralfate, metal cations such as iron, and multivitamins preparations with zinc or didanosine may substantially interfere with the gastrointestinal absorption of levofloxacin, resulting in systemic levels considerably lower than desired. These agents should be taken at least two hours before or two hours after oral LEVAQUIN® administration.

LEVAQUIN® Injection

There are no data concerning an interaction of intravenous fluoroquinolones with oral antacids, sucralfate, multivitamins, didanosine, or metal cations. However, no fluoroquinolone should be co-administered with any solution containing multivalent cations, e.g., magnesium, through the same intravenous line [see Dosage and Administration (2.5)].

7.2 Warfarin

No significant effect of LEVAQUIN® on the peak plasma concentrations, AUC, and other disposition parameters for R- and S- warfarin was detected in a clinical study involving healthy volunteers. Similarly, no apparent effect of warfarin on levofloxacin absorption and disposition was observed. However, there have been reports during the postmarketing experience in patients that LEVAQUIN® enhances the effects of warfarin. Elevations of the prothrombin time in the setting of concurrent warfarin and LEVAQUIN® use have been associated with episodes of bleeding. Prothrombin time, International Normalized Ratio (INR), or other suitable anticoagulation tests should be closely monitored if LEVAQUIN® is administered concomitantly with warfarin. Patients should also be monitored for evidence of bleeding [see Adverse Reactions (6.3); Patient Counseling Information (17.4)].

7.3 Antidiabetic Agents

Disturbances of blood glucose, including hyperglycemia and hypoglycemia, have been reported in patients treated concomitantly with fluoroquinolones and an antidiabetic agent. Therefore, careful monitoring of blood glucose is recommended when these agents are co-administered [see Warnings and Precautions (5.11); Adverse Reactions (6.2), Patient Counseling Information (17.4)].

7.4 Non-Steroidal Anti-Inflammatory Drugs

The concomitant administration of a non-steroidal anti-inflammatory drug with a fluoroquinolone, including LEVAQUIN®, may increase the risk of CNS stimulation and convulsive seizures [see Warnings and Precautions (5.6)].

7.5 Theophylline

No significant effect of LEVAQUIN® on the plasma concentrations, AUC, and other disposition parameters for theophylline was detected in a clinical study involving healthy volunteers. Similarly, no apparent effect of theophylline on levofloxacin absorption and disposition was observed. However, concomitant administration of other fluoroquinolones with theophylline has resulted in prolonged elimination half-life, elevated serum theophylline levels, and a subsequent increase in the risk of theophylline-related adverse reactions in the patient population. Therefore, theophylline levels should be closely monitored and appropriate dosage adjustments made when LEVAQUIN® is co-administered. Adverse reactions, including seizures, may occur with or without an elevation in serum theophylline levels [see Warnings and Precautions (5.6)].

7.6 Cyclosporine

No significant effect of LEVAQUIN® on the peak plasma concentrations, AUC, and other disposition parameters for cyclosporine was detected in a clinical study involving healthy volunteers. However, elevated serum levels of cyclosporine have been reported in the patient population when co-administered with some other fluoroquinolones. Levofloxacin Cmax and ke were slightly lower while Tmax and t½ were slightly longer in the presence of cyclosporine than those observed in other studies without concomitant medication. The differences, however, are not considered to be clinically significant. Therefore, no dosage adjustment is required for LEVAQUIN® or cyclosporine when administered concomitantly.

7.7 Digoxin

No significant effect of LEVAQUIN® on the peak plasma concentrations, AUC, and other disposition parameters for digoxin was detected in a clinical study involving healthy volunteers. Levofloxacin absorption and disposition kinetics were similar in the presence or absence of digoxin. Therefore, no dosage adjustment for LEVAQUIN® or digoxin is required when administered concomitantly.

7.8 Probenecid and Cimetidine

No significant effect of probenecid or cimetidine on the Cmax of levofloxacin was observed in a clinical study involving healthy volunteers. The AUC and t½ of levofloxacin were higher while CL/F and CLR were lower during concomitant treatment of LEVAQUIN® with probenecid or cimetidine compared to LEVAQUIN® alone. However, these changes do not warrant dosage adjustment for LEVAQUIN® when probenecid or cimetidine is co-administered.

7.9 Interactions with Laboratory or Diagnostic Testing

Some fluoroquinolones, including LEVAQUIN®, may produce false-positive urine screening results for opiates using commercially available immunoassay kits. Confirmation of positive opiate screens by more specific methods may be necessary.

8 USE IN SPECIFIC POPULATIONS

8.1 Pregnancy

TERATOGENIC EFFECTS

Pregnancy Category C. Levofloxacin was not teratogenic in rats at oral doses as high as 810 mg/kg/day which corresponds to 9.4 times the highest recommended human dose based upon relative body surface area, or at intravenous doses as high as 160 mg/kg/day corresponding to 1.9 times the highest recommended human dose based upon relative body surface area. The oral dose of 810 mg/kg/day to rats caused decreased fetal body weight and increased fetal mortality. No teratogenicity was observed when rabbits were dosed orally as high as 50 mg/kg/day which corresponds to 1.1 times the highest recommended human dose based upon relative body surface area, or when dosed intravenously as high as 25 mg/kg/day, corresponding to 0.5 times the highest recommended human dose based upon relative body surface area.

There are, however, no adequate and well-controlled studies in pregnant women. LEVAQUIN® should be used during pregnancy only if the potential benefit justifies the potential risk to the fetus.

8.3 Nursing Mothers

Based on data on other fluoroquinolones and very limited data on LEVAQUIN®, it can be presumed that levofloxacin will be excreted in human milk. Because of the potential for serious adverse reactions from LEVAQUIN® in nursing infants, a decision should be made whether to discontinue nursing or to discontinue the drug, taking into account the importance of the drug to the mother.

8.4 Pediatric Use

Quinolones, including levofloxacin, cause arthropathy and osteochondrosis in juvenile animals of several species. [see Warnings and Precautions (5.10) and Animal Toxicology and/or Pharmacology (13.2)].

Inhalational Anthrax (Post-Exposure)

Levofloxacin is indicated in pediatric patients for inhalational anthrax (post-exposure). The risk-benefit assessment indicates that administration of levofloxacin to pediatric patients is appropriate. The safety of levofloxacin in pediatric patients treated for more than 14 days has not been studied. The pharmacokinetics of levofloxacin following a single intravenous dose were investigated in pediatric patients ranging in age from six months to 16 years. Pediatric patients cleared levofloxacin faster than adult patients resulting in lower plasma exposures than adults for a given mg/kg dose [see Indications and Usage (1.13), Dosage and Administration (2.2), Clinical Pharmacology (12.3) and Clinical Studies (14.9)].

Adverse Events

In clinical trials, 1534 children (6 months to 16 years of age) were treated with oral and intravenous LEVAQUIN®. Children 6 months to 5 years of age received LEVAQUIN® 10 mg/kg twice a day and children greater than 5 years of age received 10 mg/kg once a day (maximum 500 mg per day) for approximately 10 days.

A subset of children in the clinical trials (1340 LEVAQUIN®-treated and 893 non-fluoroquinolone-treated) enrolled in a prospective, long-term surveillance study to assess the incidence of protocol-defined musculoskeletal disorders (arthralgia, arthritis, tendinopathy, gait abnormality) during 60 days and 1 year following the first dose of the study drug. Children treated with LEVAQUIN® had a significantly higher incidence of musculoskeletal disorders when compared to the non-fluoroquinolone-treated children as illustrated in Table 9.

Table 9: Incidence of Musculoskeletal Disorders in Pediatric Clinical Trial
Follow-up Period | LEVAQUIN® N = 1340 | Non-Fluoroquinolone [Non-Fluoroquinolone: ceftriaxone, amoxicillin/ clavulanate, clarithromycin] N = 893 | p-value [2-sided Fisher's Exact Test]
60 days | 28 (2.1%) | 8 (0.9%) | p = 0.038
1 year [There were 1199 LEVAQUIN®-treated and 804 non-fluoroquinolone-treated children who had a one-year evaluation visit. However, the incidence of musculoskeletal disorders was calculated using all reported events during the specified period for all children enrolled regardless of whether they completed the 1-year evaluation visit.] | 46 (3.4%) | 16 (1.8%) | p = 0.025

Arthralgia was the most frequently occurring musculoskeletal disorder in both treatment groups. Most of the musculoskeletal disorders in both groups involved multiple weight-bearing joints. Disorders were moderate in 8/46 (17%) children and mild in 35/46 (76%) LEVAQUIN®-treated children and most were treated with analgesics. The median time to resolution was 7 days for LEVAQUIN®-treated children and 9 for non-fluoroquinolone-treated children (approximately 80% resolved within 2 months in both groups). No child had a severe or serious disorder and all musculoskeletal disorders resolved without sequelae.

Vomiting and diarrhea were the most frequently reported adverse events, occurring in similar frequency in the LEVAQUIN®-treated and non-fluoroquinolone-treated children.

In addition to the events reported in pediatric patients in clinical trials, events reported in adults during clinical trials or post-marketing experience [see Adverse Reactions (6)] may also be expected to occur in pediatric patients.

8.5 Geriatric Use

Geriatric patients are at increased risk for developing severe tendon disorders including tendon rupture when being treated with a fluoroquinolone such as LEVAQUIN®. This risk is further increased in patients receiving concomitant corticosteroid therapy. Tendinitis or tendon rupture can involve the Achilles, hand, shoulder, or other tendon sites and can occur during or after completion of therapy; cases occurring up to several months after fluoroquinolone treatment have been reported. Caution should be used when prescribing LEVAQUIN® to elderly patients especially those on corticosteroids. Patients should be informed of this potential side effect and advised to discontinue LEVAQUIN® and contact their healthcare provider if any symptoms of tendinitis or tendon rupture occur [see Boxed Warning; Warnings and Precautions (5.1); and Adverse Reactions (6.3)].

In phase 3 clinical trials, 1,945 LEVAQUIN®-treated patients (26%) were ≥ 65 years of age. Of these, 1,081 patients (14%) were between the ages of 65 and 74 and 864 patients (12%) were 75 years or older. No overall differences in safety or effectiveness were observed between these subjects and younger subjects, but greater sensitivity of some older individuals cannot be ruled out.

Severe, and sometimes fatal, cases of hepatotoxicity have been reported post-marketing in association with LEVAQUIN®. The majority of fatal hepatotoxicity reports occurred in patients 65 years of age or older and most were not associated with hypersensitivity. LEVAQUIN® should be discontinued immediately if the patient develops signs and symptoms of hepatitis [see Warnings and Precautions (5.5)].

Elderly patients may be more susceptible to drug-associated effects on the QT interval. Therefore, precaution should be taken when using LEVAQUIN® with concomitant drugs that can result in prolongation of the QT interval (e.g., Class IA or Class III antiarrhythmics) or in patients with risk factors for torsade de pointes (e.g., known QT prolongation, uncorrected hypokalemia) [see Warnings and Precautions (5.9)].

The pharmacokinetic properties of levofloxacin in younger adults and elderly adults do not differ significantly when creatinine clearance is taken into consideration. However, since the drug is known to be substantially excreted by the kidney, the risk of toxic reactions to this drug may be greater in patients with impaired renal function. Because elderly patients are more likely to have decreased renal function, care should be taken in dose selection, and it may be useful to monitor renal function [see Clinical Pharmacology (12.3)].

8.6 Renal Impairment

Clearance of levofloxacin is substantially reduced and plasma elimination half-life is substantially prolonged in patients with impaired renal function (creatinine clearance < 50 mL/min), requiring dosage adjustment in such patients to avoid accumulation. Neither hemodialysis nor continuous ambulatory peritoneal dialysis (CAPD) is effective in removal of levofloxacin from the body, indicating that supplemental doses of LEVAQUIN® are not required following hemodialysis or CAPD [see Dosage and Administration (2.3)].

8.7 Hepatic Impairment

Pharmacokinetic studies in hepatically impaired patients have not been conducted. Due to the limited extent of levofloxacin metabolism, the pharmacokinetics of levofloxacin are not expected to be affected by hepatic impairment.

10 OVERDOSAGE

In the event of an acute overdosage, the stomach should be emptied. The patient should be observed and appropriate hydration maintained. Levofloxacin is not efficiently removed by hemodialysis or peritoneal dialysis.

LEVAQUIN® exhibits a low potential for acute toxicity. Mice, rats, dogs and monkeys exhibited the following clinical signs after receiving a single high dose of LEVAQUIN®: ataxia, ptosis, decreased locomotor activity, dyspnea, prostration, tremors, and convulsions. Doses in excess of 1500 mg/kg orally and 250 mg/kg IV produced significant mortality in rodents.

11 DESCRIPTION

LEVAQUIN® is a synthetic broad-spectrum antibacterial agent for oral and intravenous administration. Chemically, levofloxacin, a chiral fluorinated carboxyquinolone, is the pure (-)-(S)-enantiomer of the racemic drug substance ofloxacin. The chemical name is (-)-(S)-9-fluoro-2,3-dihydro-3-methyl-10-(4-methyl-1-piperazinyl)-7-oxo-7H-pyrido[1,2,3-de]-1,4-benzoxazine-6-carboxylic acid hemihydrate.

Figure 1: The Chemical Structure of Levofloxacin

The empirical formula is C18H20FN3O4 • ½ H2O and the molecular weight is 370.38. Levofloxacin is a light yellowish-white to yellow-white crystal or crystalline powder. The molecule exists as a zwitterion at the pH conditions in the small intestine.

The data demonstrate that from pH 0.6 to 5.8, the solubility of levofloxacin is essentially constant (approximately 100 mg/mL). Levofloxacin is considered soluble to freely soluble in this pH range, as defined by USP nomenclature. Above pH 5.8, the solubility increases rapidly to its maximum at pH 6.7 (272 mg/mL) and is considered freely soluble in this range. Above pH 6.7, the solubility decreases and reaches a minimum value (about 50 mg/mL) at a pH of approximately 6.9.

Levofloxacin has the potential to form stable coordination compounds with many metal ions. This in vitro chelation potential has the following formation order: Al^+3>Cu^+2>Zn^+2>Mg^+2>Ca^+2.

Excipients and Description of Dosage Forms

LEVAQUIN® Tablets

LEVAQUIN® Tablets are available as film-coated tablets and contain the following inactive ingredients:

- 250 mg (as expressed in the anhydrous form): hypromellose, crospovidone, microcrystalline cellulose, magnesium stearate, polyethylene glycol, titanium dioxide, polysorbate 80 and synthetic red iron oxide.
- 500 mg (as expressed in the anhydrous form): hypromellose, crospovidone, microcrystalline cellulose, magnesium stearate, polyethylene glycol, titanium dioxide, polysorbate 80 and synthetic red and yellow iron oxides.
- 750 mg (as expressed in the anhydrous form): hypromellose, crospovidone, microcrystalline cellulose, magnesium stearate, polyethylene glycol, titanium dioxide, polysorbate 80.

LEVAQUIN® Oral Solution

LEVAQUIN® Oral Solution, 25 mg/mL, is a multi-use self-preserving aqueous solution of levofloxacin with pH ranging from 5.0 to 6.0. The appearance of LEVAQUIN® Oral Solution may range from clear yellow to clear greenish-yellow. This does not adversely affect product potency.

LEVAQUIN® Oral Solution contains the following inactive ingredients: sucrose, glycerin, sucralose, hydrochloric acid, purified water, propylene glycol, artificial and natural flavors, benzyl alcohol, ascorbic acid, and caramel color. It may also contain a solution of sodium hydroxide for pH adjustment.

LEVAQUIN® Injection

The appearance of LEVAQUIN® Injection may range from a clear yellow to a clear greenish-yellow solution. This does not adversely affect product potency.

LEVAQUIN® Injection in Single-Use Vials is a sterile, preservative-free aqueous solution of levofloxacin in Water for Injection, with pH ranging from 3.8 to 5.8.

LEVAQUIN® Injection Premix in Single-Use Flexible Containers is a sterile, preservative-free aqueous solution of levofloxacin with pH ranging from 3.8 to 5.8. This is a dilute, non-pyrogenic, nearly isotonic premixed solution that contains levofloxacin in 5% Dextrose (D5W). Solutions of hydrochloric acid and sodium hydroxide may have been added to adjust the pH.

The flexible container is fabricated from a specially formulated non-plasticized, thermoplastic copolyester (CR3). The amount of water that can permeate from the container into the overwrap is insufficient to affect the solution significantly. Solutions in contact with the flexible container can leach out certain of the container's chemical components in very small amounts within the expiration period. The suitability of the container material has been confirmed by tests in animals according to USP biological tests for plastic containers.

12 CLINICAL PHARMACOLOGY

12.1 Mechanism of Action

Levofloxacin is a member of the fluoroquinolone class of antibacterial agents [see Clinical Pharmacology (12.4)].

12.3 Pharmacokinetics

The mean ± SD pharmacokinetic parameters of levofloxacin determined under single and steady-state conditions following oral tablet, oral solution, or intravenous (IV) doses of LEVAQUIN® are summarized in Table 10.

Table 10: Mean ± SD Levofloxacin PK Parameters
Regimen | Cmax | Tmax | AUC | CL/F [clearance/bioavailability] | Vd/F [volume of distribution/bioavailability] | t1/2 | CLR
Regimen | (mcg/mL) | (h) | (mcg∙h/mL) | (mL/min) | (L) | (h) | (mL/min)
Single dose
250 mg oral tablet [healthy males 18–53 years of age] | 2.8 ± 0.4 | 1.6 ± 1.0 | 27.2 ± 3.9 | 156 ± 20 | ND | 7.3 ± 0.9 | 142 ± 21
500 mg oral tablet [Absolute bioavailability; F=0.99 ± 0.08 from a 500 mg tablet and F=0.99 ± 0.06 from a 750 mg tablet;] | 5.1 ± 0.8 | 1.3 ± 0.6 | 47.9 ± 6.8 | 178 ± 28 | ND | 6.3 ± 0.6 | 103 ± 30
500 mg oral solution [healthy males and females 19–55 years of age.] | 5.8 ± 1.8 | 0.8 ± 0.7 | 47.8 ± 10.8 | 183 ± 40 | 112 ± 37.2 | 7.0 ± 1.4 | ND
500 mg IV | 6.2 ± 1.0 | 1.0 ± 0.1 | 48.3 ± 5.4 | 175 ± 20 | 90 ± 11 | 6.4 ± 0.7 | 112 ± 25
750 mg oral tablet [healthy male and female subjects 18–54 years of age] | 9.3 ± 1.6 | 1.6 ± 0.8 | 101 ± 20 | 129 ± 24 | 83 ± 17 | 7.5 ± 0.9 | ND
750 mg IV | 11.5 ± 4.0 [60 min infusion for 250 mg and 500 mg doses, 90 min infusion for 750 mg dose] | ND | 110 ± 40 | 126 ± 39 | 75 ± 13 | 7.5 ± 1.6 | ND
Multiple dose
500 mg every 24h oral tablet | 5.7 ± 1.4 | 1.1 ± 0.4 | 47.5 ± 6.7 | 175 ± 25 | 102 ± 22 | 7.6 ± 1.6 | 116 ± 31
500 mg every 24h IV | 6.4 ± 0.8 | ND | 54.6 ± 11.1 | 158 ± 29 | 91 ± 12 | 7.0 ± 0.8 | 99 ± 28
500 mg or 250 mg every 24h IV, patients with bacterial infection [500 mg every 48h for patients with moderate renal impairment (CLCR 20–50 mL/min) and infections of the respiratory tract or skin] | 8.7± 4.0 [dose-normalized values (to 500 mg dose), estimated by population pharmacokinetic modeling] | ND | 72.5 ± 51.2 | 154 ± 72 | 111 ± 58 | ND | ND
750 mg every 24h oral tablet | 8.6 ± 1.9 | 1.4 ± 0.5 | 90.7 ± 17.6 | 143 ± 29 | 100 ± 16 | 8.8 ± 1.5 | 116 ± 28
750 mg every 24h IV | 12.1 ± 4.1 | ND | 108 ± 34 | 126 ± 37 | 80 ± 27 | 7.9 ± 1.9 | ND
500 mg oral tablet single dose, effects of gender and age:
Male [healthy males 22–75 years of age] | 5.5 ± 1.1 | 1.2 ± 0.4 | 54.4 ± 18.9 | 166 ± 44 | 89 ± 13 | 7.5 ± 2.1 | 126 ± 38
Female [healthy females 18–80 years of age] | 7.0 ± 1.6 | 1.7 ± 0.5 | 67.7 ± 24.2 | 136 ± 44 | 62 ± 16 | 6.1 ± 0.8 | 106 ± 40
Young [young healthy male and female subjects 18–36 years of age] | 5.5 ± 1.0 | 1.5 ± 0.6 | 47.5 ± 9.8 | 182 ± 35 | 83 ± 18 | 6.0 ± 0.9 | 140 ± 33
Elderly [healthy elderly male and female subjects 66–80 years of age] | 7.0 ± 1.6 | 1.4 ± 0.5 | 74.7 ± 23.3 | 121 ± 33 | 67 ± 19 | 7.6 ± 2.0 | 91 ± 29
500 mg oral single dose tablet, patients with renal insufficiency:
CLCR 50–80 mL/min | 7.5 ± 1.8 | 1.5 ± 0.5 | 95.6 ± 11.8 | 88 ± 10 | ND | 9.1 ± 0.9 | 57 ± 8
CLCR 20–49 mL/min | 7.1 ± 3.1 | 2.1 ± 1.3 | 182.1 ± 62.6 | 51 ± 19 | ND | 27 ± 10 | 26 ± 13
CLCR <20 mL/min | 8.2 ± 2.6 | 1.1 ± 1.0 | 263.5 ± 72.5 | 33 ± 8 | ND | 35 ± 5 | 13 ± 3
Hemodialysis | 5.7 ± 1.0 | 2.8 ± 2.2 | ND | ND | ND | 76 ± 42 | ND
CAPD | 6.9 ± 2.3 | 1.4 ± 1.1 | ND | ND | ND | 51 ± 24 | ND
ND=not determined.

Absorption

Levofloxacin is rapidly and essentially completely absorbed after oral administration. Peak plasma concentrations are usually attained one to two hours after oral dosing. The absolute bioavailability of levofloxacin from a 500 mg tablet and a 750 mg tablet of LEVAQUIN® are both approximately 99%, demonstrating complete oral absorption of levofloxacin. Following a single intravenous dose of LEVAQUIN® to healthy volunteers, the mean ± SD peak plasma concentration attained was 6.2 ± 1.0 mcg/mL after a 500 mg dose infused over 60 minutes and 11.5 ± 4.0 mcg/mL after a 750 mg dose infused over 90 minutes. LEVAQUIN® Oral Solution and Tablet formulations are bioequivalent.

Levofloxacin pharmacokinetics are linear and predictable after single and multiple oral or IV dosing regimens. Steady-state conditions are reached within 48 hours following a 500 mg or 750 mg once-daily dosage regimen. The mean ± SD peak and trough plasma concentrations attained following multiple once-daily oral dosage regimens were approximately 5.7 ± 1.4 and 0.5 ± 0.2 mcg/mL after the 500 mg doses, and 8.6 ± 1.9 and 1.1 ± 0.4 mcg/mL after the 750 mg doses, respectively. The mean ± SD peak and trough plasma concentrations attained following multiple once-daily IV regimens were approximately 6.4 ± 0.8 and 0.6 ± 0.2 mcg/mL after the 500 mg doses, and 12.1 ± 4.1 and 1.3 ± 0.71 mcg/mL after the 750 mg doses, respectively. Oral administration of a 500 mg dose of LEVAQUIN® with food prolongs the time to peak concentration by approximately 1 hour and decreases the peak concentration by approximately 14% following tablet and approximately 25% following oral solution administration. Therefore, LEVAQUIN® Tablets can be administered without regard to food. It is recommended that LEVAQUIN® Oral Solution be taken 1 hour before or 2 hours after eating.

The plasma concentration profile of levofloxacin after IV administration is similar and comparable in extent of exposure (AUC) to that observed for LEVAQUIN® Tablets when equal doses (mg/mg) are administered. Therefore, the oral and IV routes of administration can be considered interchangeable (see Figure 2 and Figure 3).

Figure 2: Mean Levofloxacin Plasma Concentration vs. Time Profile: 750 mg

Figure 3: Mean Levofloxacin Plasma Concentration vs. Time Profile: 500 mg

Distribution

The mean volume of distribution of levofloxacin generally ranges from 74 to 112 L after single and multiple 500 mg or 750 mg doses, indicating widespread distribution into body tissues. Levofloxacin reaches its peak levels in skin tissues and in blister fluid of healthy subjects at approximately 3 hours after dosing. The skin tissue biopsy to plasma AUC ratio is approximately 2 and the blister fluid to plasma AUC ratio is approximately 1 following multiple once-daily oral administration of 750 mg and 500 mg doses of LEVAQUIN®, respectively, to healthy subjects. Levofloxacin also penetrates well into lung tissues. Lung tissue concentrations were generally 2- to 5-fold higher than plasma concentrations and ranged from approximately 2.4 to 11.3 mcg/g over a 24-hour period after a single 500 mg oral dose.

In vitro, over a clinically relevant range (1 to 10 mcg/mL) of serum/plasma levofloxacin concentrations, levofloxacin is approximately 24 to 38% bound to serum proteins across all species studied, as determined by the equilibrium dialysis method. Levofloxacin is mainly bound to serum albumin in humans. Levofloxacin binding to serum proteins is independent of the drug concentration.

Metabolism

Levofloxacin is stereochemically stable in plasma and urine and does not invert metabolically to its enantiomer, D-ofloxacin. Levofloxacin undergoes limited metabolism in humans and is primarily excreted as unchanged drug in the urine. Following oral administration, approximately 87% of an administered dose was recovered as unchanged drug in urine within 48 hours, whereas less than 4% of the dose was recovered in feces in 72 hours. Less than 5% of an administered dose was recovered in the urine as the desmethyl and N-oxide metabolites, the only metabolites identified in humans. These metabolites have little relevant pharmacological activity.

Excretion

Levofloxacin is excreted largely as unchanged drug in the urine. The mean terminal plasma elimination half-life of levofloxacin ranges from approximately 6 to 8 hours following single or multiple doses of levofloxacin given orally or intravenously. The mean apparent total body clearance and renal clearance range from approximately 144 to 226 mL/min and 96 to 142 mL/min, respectively. Renal clearance in excess of the glomerular filtration rate suggests that tubular secretion of levofloxacin occurs in addition to its glomerular filtration. Concomitant administration of either cimetidine or probenecid results in approximately 24% and 35% reduction in the levofloxacin renal clearance, respectively, indicating that secretion of levofloxacin occurs in the renal proximal tubule. No levofloxacin crystals were found in any of the urine samples freshly collected from subjects receiving LEVAQUIN®.

Geriatric

There are no significant differences in levofloxacin pharmacokinetics between young and elderly subjects when the subjects' differences in creatinine clearance are taken into consideration. Following a 500 mg oral dose of LEVAQUIN® to healthy elderly subjects (66 – 80 years of age), the mean terminal plasma elimination half-life of levofloxacin was about 7.6 hours, as compared to approximately 6 hours in younger adults. The difference was attributable to the variation in renal function status of the subjects and was not believed to be clinically significant. Drug absorption appears to be unaffected by age. LEVAQUIN® dose adjustment based on age alone is not necessary [see Use in Specific Populations (8.5)].

Pediatrics

The pharmacokinetics of levofloxacin following a single 7 mg/kg intravenous dose were investigated in pediatric patients ranging in age from 6 months to 16 years. Pediatric patients cleared levofloxacin faster than adult patients, resulting in lower plasma exposures than adults for a given mg/kg dose. Subsequent pharmacokinetic analyses predicted that a dosage regimen of 8 mg/kg every 12 hours (not to exceed 250 mg per dose) for pediatric patients 6 months to 17 years of age would achieve comparable steady state plasma exposures (AUC0–24 and Cmax) to those observed in adult patients administered 500 mg of levofloxacin once every 24 hours.

Gender

There are no significant differences in levofloxacin pharmacokinetics between male and female subjects when subjects' differences in creatinine clearance are taken into consideration. Following a 500 mg oral dose of LEVAQUIN® to healthy male subjects, the mean terminal plasma elimination half-life of levofloxacin was about 7.5 hours, as compared to approximately 6.1 hours in female subjects. This difference was attributable to the variation in renal function status of the male and female subjects and was not believed to be clinically significant. Drug absorption appears to be unaffected by the gender of the subjects. Dose adjustment based on gender alone is not necessary.

Race

The effect of race on levofloxacin pharmacokinetics was examined through a covariate analysis performed on data from 72 subjects: 48 white and 24 non-white. The apparent total body clearance and apparent volume of distribution were not affected by the race of the subjects.

Renal Impairment

Clearance of levofloxacin is substantially reduced and plasma elimination half-life is substantially prolonged in adult patients with impaired renal function (creatinine clearance < 50 mL/min), requiring dosage adjustment in such patients to avoid accumulation. Neither hemodialysis nor continuous ambulatory peritoneal dialysis (CAPD) is effective in removal of levofloxacin from the body, indicating that supplemental doses of LEVAQUIN® are not required following hemodialysis or CAPD [see Dosage and Administration (2.3), Use in Specific Populations (8.6)].

Hepatic Impairment

Pharmacokinetic studies in hepatically impaired patients have not been conducted. Due to the limited extent of levofloxacin metabolism, the pharmacokinetics of levofloxacin are not expected to be affected by hepatic impairment [see Use in Specific Populations (8.7)].

Bacterial Infection

The pharmacokinetics of levofloxacin in patients with serious community-acquired bacterial infections are comparable to those observed in healthy subjects.

Drug-Drug Interactions

The potential for pharmacokinetic drug interactions between LEVAQUIN® and antacids, warfarin, theophylline, cyclosporine, digoxin, probenecid, and cimetidine has been evaluated [see Drug Interactions (7)].

12.4 Microbiology

Mechanism of Action

Levofloxacin is the L-isomer of the racemate, ofloxacin, a quinolone antimicrobial agent. The antibacterial activity of ofloxacin resides primarily in the L-isomer. The mechanism of action of levofloxacin and other fluoroquinolone antimicrobials involves inhibition of bacterial topoisomerase IV and DNA gyrase (both of which are type II topoisomerases), enzymes required for DNA replication, transcription, repair and recombination.

Drug Resistance

Fluoroquinolone resistance can arise through mutations in defined regions of DNA gyrase or topoisomerase IV, termed the Quinolone-Resistance Determining Regions (QRDRs), or through altered efflux.

Fluoroquinolones, including levofloxacin, differ in chemical structure and mode of action from aminoglycosides, macrolides and β-lactam antibiotics, including penicillins. Fluoroquinolones may, therefore, be active against bacteria resistant to these antimicrobials.

Resistance to levofloxacin due to spontaneous mutation in vitro is a rare occurrence (range: 10^-9 to 10^-10). Although cross-resistance has been observed between levofloxacin and some other fluoroquinolones, some microorganisms resistant to other fluoroquinolones may be susceptible to levofloxacin.

Activity in vitro and in vivo

Levofloxacin has in vitro activity against a wide range of Gram-negative and Gram-positive microorganisms.

Levofloxacin is often bactericidal at concentrations equal to or slightly greater than inhibitory concentrations.

Levofloxacin has been shown to be active against most strains of the following microorganisms both in vitro and in clinical infections as described in Indications and Usage (1):

Aerobic Gram-Positive Microorganisms
  Enterococcus faecalis (many strains are only moderately susceptible)
  Staphylococcus aureus (methicillin-susceptible strains)
  Staphylococcus epidermidis (methicillin-susceptible strains)
  Staphylococcus saprophyticus
  Streptococcus pneumoniae (including multi-drug resistant strains [MDRSP] [MDRSP (Multi-drug resistant Streptococcus pneumoniae) isolates are strains resistant to two or more of the following antibiotics: penicillin (MIC ≥2 mcg/mL), 2nd generation cephalosporins, e.g., cefuroxime; macrolides, tetracyclines and trimethoprim/sulfamethoxazole.])
  Streptococcus pyogenes

Aerobic Gram-Negative Microorganisms
  Enterobacter cloacae
  Escherichia coli
  Haemophilus influenzae
  Haemophilus parainfluenzae
  Klebsiella pneumoniae
  Legionella pneumophila
  Moraxella catarrhalis
  Proteus mirabilis
  Pseudomonas aeruginosa [As with other drugs in this class, some strains of Pseudomonas aeruginosa may develop resistance fairly rapidly during treatment with LEVAQUIN®.]
  Serratia marcescens

Other Microorganisms
  Chlamydophila pneumoniae
  Mycoplasma pneumoniae

Levofloxacin has been shown to be active against Bacillus anthracis both in vitro and by use of plasma levels as a surrogate marker in a rhesus monkey model for anthrax (post-exposure) [see Indications and Usage (1.13), Clinical Studies (14.9)].

The following in vitro data are available, but their clinical significance is unknown: Levofloxacin exhibits in vitro minimum inhibitory concentrations (MIC values) of 2 mcg/mL or less against most (≥90%) strains of the following microorganisms; however, the safety and effectiveness of LEVAQUIN® in treating clinical infections due to these microorganisms have not been established in adequate and well-controlled trials.

Aerobic Gram-Positive Microorganisms
  Staphylococcus haemolyticus
  β-hemolytic Streptococcus (Group C/F)
  β-hemolytic Streptococcus (Group G)
  Streptococcus agalactiae
  Streptococcus milleri
  Viridans group streptococci

Aerobic Gram-Negative Microorganisms
  Acinetobacter baumannii
  Acinetobacter lwoffii
  Bordetella pertussis
  Citrobacter koseri
  Citrobacter freundii
  Enterobacter aerogenes
  Enterobacter sakazakii
  Klebsiella oxytoca
  Morganella morganii
  Pantoea agglomerans
  Proteus vulgaris
  Providencia rettgeri
  Providencia stuartii
  Pseudomonas fluorescens

Anaerobic Gram-Positive Microorganisms
  Clostridium perfringens

Susceptibility Tests

Susceptibility testing for levofloxacin should be performed, as it is the optimal predictor of activity.

- Dilution techniques:

Quantitative methods are used to determine antimicrobial minimal inhibitory concentrations (MIC values). These MIC values provide estimates of the susceptibility of bacteria to antimicrobial compounds. The MIC values should be determined using a standardized procedure. Standardized procedures are based on a dilution method^1 (broth or agar) or equivalent with standardized inoculum concentrations and standardized concentrations of levofloxacin powder. The MIC values should be interpreted according to the criteria outlined in Table 11.

- Diffusion techniques:

Quantitative methods that require measurement of zone diameters also provide reproducible estimates of the susceptibility of bacteria to antimicrobial compounds. One such standardized procedure^2 requires the use of standardized inoculum concentrations. This procedure uses paper disks impregnated with 5 mcg levofloxacin to test the susceptibility of microorganisms to levofloxacin.

Reports from the laboratory providing results of the standard single-disk susceptibility test with a 5 mcg levofloxacin disk should be interpreted according to the criteria outlined in Table 11. Interpretation involves correlation of the diameter obtained in the disk test with the MIC for levofloxacin.

Table 11: Susceptibility Interpretive Criteria for LEVAQUIN®
 | Minimum Inhibitory Concentrations (mcg/mL) |  |  | Disk Diffusion (zone diameter in mm)
Pathogen | S | I | R | S | I | R
Enterobacteriaceae | ≤2 | 4 | ≥8 | ≥17 | 14–16 | ≤13
Enterococcus faecalis | ≤2 | 4 | ≥8 | ≥17 | 14–16 | ≤13
Methicillin-susceptible Staphylococcus species | ≤2 | 4 | ≥8 | ≥17 | 14–16 | ≤13
Pseudomonas aeruginosa | ≤2 | 4 | ≥8 | ≥17 | 14–16 | ≤13
Haemophilus influenzae | ≤2 [These interpretive standards are applicable only to broth microdilution susceptibility testing with Haemophilus influenzae and Haemophilus parainfluenzae using Haemophilus Test Medium.^1] | -- [The current absence of data on resistant strains precludes defining any categories other than "Susceptible." Strains yielding MIC /zone diameter results suggestive of a "nonsusceptible" category should be submitted to a reference laboratory for further testing.] | -- | ≥17 [These interpretive standards are applicable only to disk diffusion susceptibility testing with Haemophilus influenzae and Haemophilus parainfluenzae using Haemophilus Test Medium.^2] | -- | --
Haemophilus parainfluenzae | ≤2 | -- | -- | ≥17 | -- | --
Streptococcus pneumoniae | ≤2 [These interpretive standards are applicable only to broth microdilution susceptibility tests using cation-adjusted Mueller-Hinton broth with 2–5% lysed horse blood.] | 4 | ≥8 | ≥17 [These zone diameter standards for Streptococcus spp. including S. pneumoniae apply only to tests performed using Mueller-Hinton agar supplemented with 5% sheep blood and incubated in 5% CO2.] | 14–16 | ≤13
Streptococcus pyogenes | ≤2 | 4 | ≥8 | ≥17 | 14–16 | ≤13
S = Susceptible, I = Intermediate, R = Resistant

A report of Susceptible indicates that the pathogen is likely to be inhibited if the antimicrobial compound in the blood reaches the concentrations usually achievable. A report of Intermediate indicates that the result should be considered equivocal, and, if the microorganism is not fully susceptible to alternative, clinically feasible drugs, the test should be repeated. This category implies possible clinical applicability in body sites where the drug is physiologically concentrated or in situations where a high dosage of drug can be used. This category also provides a buffer zone which prevents small uncontrolled technical factors from causing major discrepancies in interpretation. A report of Resistant indicates that the pathogen is not likely to be inhibited if the antimicrobial compound in the blood reaches the concentrations usually achievable; other therapy should be selected.

- Quality Control:

Standardized susceptibility test procedures require the use of laboratory control microorganisms to control the technical aspects of the laboratory procedures. For dilution technique, standard levofloxacin powder should give the MIC values provided in Table 12. For diffusion technique, the 5 mcg levofloxacin disk should provide zone diameters provided in Table 12.

Table 12: Quality Control for Susceptibility Testing
Microorganism | Microorganism QC Number | MIC (mcg/mL) | Disk Diffusion (zone diameter in mm)
Enterococcus faecalis | ATCC 29212 | 0.25 – 2 | --
Escherichia coli | ATCC 25922 | 0.008 – 0.06 | 29 – 37
Escherichia coli [Careful maintenance of this organism is required as the strain may lose its plasmid.] | ATCC 35218 | 0.015 – 0.06 | --
Haemophilus influenzae | ATCC 49247 | 0.008 – 0.03 [This quality control range is applicable to only H. influenzae ATCC 49247 tested by a broth microdilution procedure using Haemophilus Test Medium (HTM).^1] | 32 – 40 [This quality control range is applicable to only H. influenzae ATCC 49247 tested by a disk diffusion procedure using Haemophilus Test Medium (HTM).^2]
Pseudomonas aeruginosa | ATCC 27853 | 0.5 – 4 | 19 – 26
Staphylococcus aureus | ATCC 29213 | 0.06 – 0.5 | --
Staphylococcus aureus | ATCC 25923 | -- | 25 – 30
Streptococcus pneumoniae | ATCC 49619 | 0.5 – 2 [This quality control range is applicable to only S. pneumoniae ATCC 49619 tested by a broth microdilution procedure using cation-adjusted Mueller-Hinton broth with 2–5% lysed horse blood.] | 20 – 25 [This quality control range is applicable to only S. pneumoniae ATCC 49619 tested by a disk diffusion procedure using Mueller-Hinton agar supplemented with 5% sheep blood and incubated in 5% CO2.]

13 NONCLINICAL TOXICOLOGY

13.1 Carcinogenesis, Mutagenesis, Impairment of Fertility

In a lifetime bioassay in rats, levofloxacin exhibited no carcinogenic potential following daily dietary administration for 2 years; the highest dose (100 mg/kg/day) was 1.4 times the highest recommended human dose (750 mg) based upon relative body surface area. Levofloxacin did not shorten the time to tumor development of UV-induced skin tumors in hairless albino (Skh-1) mice at any levofloxacin dose level and was therefore not photo-carcinogenic under conditions of this study. Dermal levofloxacin concentrations in the hairless mice ranged from 25 to 42 mcg/g at the highest levofloxacin dose level (300 mg/kg/day) used in the photo-carcinogenicity study. By comparison, dermal levofloxacin concentrations in human subjects receiving 750 mg of LEVAQUIN® averaged approximately 11.8 mcg/g at Cmax.

Levofloxacin was not mutagenic in the following assays: Ames bacterial mutation assay (S. typhimurium and E. coli), CHO/HGPRT forward mutation assay, mouse micronucleus test, mouse dominant lethal test, rat unscheduled DNA synthesis assay, and the mouse sister chromatid exchange assay. It was positive in the in vitro chromosomal aberration (CHL cell line) and sister chromatid exchange (CHL/IU cell line) assays.

Levofloxacin caused no impairment of fertility or reproductive performance in rats at oral doses as high as 360 mg/kg/day, corresponding to 4.2 times the highest recommended human dose based upon relative body surface area and intravenous doses as high as 100 mg/kg/day, corresponding to 1.2 times the highest recommended human dose based upon relative body surface area.

13.2 Animal Toxicology and/or Pharmacology

Levofloxacin and other quinolones have been shown to cause arthropathy in immature animals of most species tested [see Warnings and Precautions (5.10)]. In immature dogs (4–5 months old), oral doses of 10 mg/kg/day for 7 days and intravenous doses of 4 mg/kg/day for 14 days of levofloxacin resulted in arthropathic lesions. Administration at oral doses of 300 mg/kg/day for 7 days and intravenous doses of 60 mg/kg/day for 4 weeks produced arthropathy in juvenile rats. Three-month old beagle dogs dosed orally with levofloxacin at 40 mg/kg/day exhibited clinically severe arthrotoxicity resulting in the termination of dosing at Day 8 of a 14-day dosing routine. Slight musculoskeletal clinical effects, in the absence of gross pathological or histopathological effects, resulted from the lowest dose level of 2.5 mg/kg/day (approximately 0.2-fold the pediatric dose based upon AUC comparisons). Synovitis and articular cartilage lesions were observed at the 10 and 40 mg/kg dose levels (approximately 0.7-fold and 2.4-fold the pediatric dose, respectively, based on AUC comparisons). Articular cartilage gross pathology and histopathology persisted to the end of the 18-week recovery period for those dogs from the 10 and 40 mg/kg/day dose levels.

When tested in a mouse ear swelling bioassay, levofloxacin exhibited phototoxicity similar in magnitude to ofloxacin, but less phototoxicity than other quinolones.

While crystalluria has been observed in some intravenous rat studies, urinary crystals are not formed in the bladder, being present only after micturition and are not associated with nephrotoxicity.

In mice, the CNS stimulatory effect of quinolones is enhanced by concomitant administration of non-steroidal anti-inflammatory drugs.

In dogs, levofloxacin administered at 6 mg/kg or higher by rapid intravenous injection produced hypotensive effects. These effects were considered to be related to histamine release.

In vitro and in vivo studies in animals indicate that levofloxacin is neither an enzyme inducer nor inhibitor in the human therapeutic plasma concentration range; therefore, no drug metabolizing enzyme-related interactions with other drugs or agents are anticipated.

14 CLINICAL STUDIES

14.1 Nosocomial Pneumonia

Adult patients with clinically and radiologically documented nosocomial pneumonia were enrolled in a multicenter, randomized, open-label study comparing intravenous LEVAQUIN® (750 mg once daily) followed by oral LEVAQUIN® (750 mg once daily) for a total of 7–15 days to intravenous imipenem/cilastatin (500–1000 mg every 6–8 hours daily) followed by oral ciprofloxacin (750 mg every 12 hours daily) for a total of 7–15 days. LEVAQUIN®-treated patients received an average of 7 days of intravenous therapy (range: 1–16 days); comparator-treated patients received an average of 8 days of intravenous therapy (range: 1–19 days).

Overall, in the clinically and microbiologically evaluable population, adjunctive therapy was empirically initiated at study entry in 56 of 93 (60.2%) patients in the LEVAQUIN® arm and 53 of 94 (56.4%) patients in the comparator arm. The average duration of adjunctive therapy was 7 days in the LEVAQUIN® arm and 7 days in the comparator. In clinically and microbiologically evaluable patients with documented Pseudomonas aeruginosa infection, 15 of 17 (88.2%) received ceftazidime (N=11) or piperacillin/tazobactam (N=4) in the LEVAQUIN® arm and 16 of 17 (94.1%) received an aminoglycoside in the comparator arm. Overall, in clinically and microbiologically evaluable patients, vancomycin was added to the treatment regimen of 37 of 93 (39.8%) patients in the LEVAQUIN® arm and 28 of 94 (29.8%) patients in the comparator arm for suspected methicillin-resistant S. aureus infection.

Clinical success rates in clinically and microbiologically evaluable patients at the posttherapy visit (primary study endpoint assessed on day 3–15 after completing therapy) were 58.1% for LEVAQUIN® and 60.6% for comparator. The 95% CI for the difference of response rates (LEVAQUIN® minus comparator) was [-17.2, 12.0]. The microbiological eradication rates at the posttherapy visit were 66.7% for LEVAQUIN® and 60.6% for comparator. The 95% CI for the difference of eradication rates (LEVAQUIN® minus comparator) was [-8.3, 20.3]. Clinical success and microbiological eradication rates by pathogen are detailed in Table 13.

Table 13: Clinical Success Rates and Microbiological Eradication Rates (Nosocomial Pneumonia)
Pathogen | N | LEVAQUIN® No. (%) of Patients Microbiologic/Clinical Outcomes | N | Imipenem/Cilastatin No. (%) of Patients Microbiologic/Clinical Outcomes
MSSA [Methicillin-susceptible S. aureus] | 21 | 14 (66.7)/13 (61.9) | 19 | 13 (68.4)/15 (78.9)
P. aeruginosa [See above text for use of combination therapy] | 17 | 10 (58.8)/11 (64.7) | 17 | 5 (29.4)/7 (41.2)
S. marcescens | 11 | 9 (81.8)/7 (63.6) | 7 | 2 (28.6)/3 (42.9)
E. coli | 12 | 10 (83.3)/7 (58.3) | 11 | 7 (63.6)/8 (72.7)
K. pneumoniae [The observed differences in rates for the clinical and microbiological outcomes may reflect other factors that were not accounted for in the study] | 11 | 9 (81.8)/5 (45.5) | 7 | 6 (85.7)/3 (42.9)
H. influenzae | 16 | 13 (81.3)/10 (62.5) | 15 | 14 (93.3)/11 (73.3)
S. pneumoniae | 4 | 3 (75.0)/3 (75.0) | 7 | 5 (71.4)/4 (57.1)

14.2 Community-Acquired Pneumonia: 7–14 day Treatment Regimen

Adult inpatients and outpatients with a diagnosis of community-acquired bacterial pneumonia were evaluated in 2 pivotal clinical studies. In the first study, 590 patients were enrolled in a prospective, multi-center, unblinded randomized trial comparing LEVAQUIN® 500 mg once daily orally or intravenously for 7 to 14 days to ceftriaxone 1 to 2 grams intravenously once or in equally divided doses twice daily followed by cefuroxime axetil 500 mg orally twice daily for a total of 7 to 14 days. Patients assigned to treatment with the control regimen were allowed to receive erythromycin (or doxycycline if intolerant of erythromycin) if an infection due to atypical pathogens was suspected or proven. Clinical and microbiologic evaluations were performed during treatment, 5 to 7 days posttherapy, and 3 to 4 weeks posttherapy. Clinical success (cure plus improvement) with LEVAQUIN® at 5 to 7 days posttherapy, the primary efficacy variable in this study, was superior (95%) to the control group (83%). The 95% CI for the difference of response rates (LEVAQUIN® minus comparator) was [-6, 19]. In the second study, 264 patients were enrolled in a prospective, multi-center, non-comparative trial of 500 mg LEVAQUIN® administered orally or intravenously once daily for 7 to 14 days. Clinical success for clinically evaluable patients was 93%. For both studies, the clinical success rate in patients with atypical pneumonia due to Chlamydophila pneumoniae, Mycoplasma pneumoniae, and Legionella pneumophila were 96%, 96%, and 70%, respectively. Microbiologic eradication rates across both studies are presented in Table 14.

Table 14: Microbiologic Eradication Rates Across 2 Community Acquired Pneumonia Clinical Studies
Pathogen | No. Pathogens | Microbiologic Eradication Rate (%)
H. influenzae | 55 | 98
S. pneumoniae | 83 | 95
S. aureus | 17 | 88
M. catarrhalis | 18 | 94
H. parainfluenzae | 19 | 95
K. pneumoniae | 10 | 100.0

Community-Acquired Pneumonia Due to Multi-Drug Resistant Streptococcus pneumoniae

LEVAQUIN® was effective for the treatment of community-acquired pneumonia caused by multi-drug resistant Streptococcus pneumoniae (MDRSP). MDRSP isolates are strains resistant to two or more of the following antibacterials: penicillin (MIC ≥2 mcg/mL), 2nd generation cephalosporins (e.g., cefuroxime, macrolides, tetracyclines and trimethoprim/sulfamethoxazole). Of 40 microbiologically evaluable patients with MDRSP isolates, 38 patients (95.0%) achieved clinical and bacteriologic success at post-therapy. The clinical and bacterial success rates are shown in Table 15.

Table 15: Clinical and Bacterial Success Rates for LEVAQUIN®-Treated MDRSP in Community Acquired Pneumonia Patients (Population Valid for Efficacy)
Screening Susceptibility | Clinical Success |  | Bacteriological Success [One patient had a respiratory isolate that was resistant to tetracycline, cefuroxime, macrolides and TMP/SMX and intermediate to penicillin and a blood isolate that was intermediate to penicillin and cefuroxime and resistant to the other classes. The patient is included in the database based on respiratory isolate.]
 | n/N [n=the number of microbiologically evaluable patients who were clinical successes; N=number of microbiologically evaluable patients in the designated resistance group.] | % | n/N [n=the number of MDRSP isolates eradicated or presumed eradicated in microbiologically evaluable patients; N=number of MDRSP isolates in a designated resistance group.] | %
Penicillin-resistant | 16/17 | 94.1 | 16/17 | 94.1
2nd generation Cephalosporin resistant | 31/32 | 96.9 | 31/32 | 96.9
Macrolide-resistant | 28/29 | 96.6 | 28/29 | 96.6
Trimethoprim/ Sulfamethoxazole resistant | 17/19 | 89.5 | 17/19 | 89.5
Tetracycline-resistant | 12/12 | 100 | 12/12 | 100

Not all isolates were resistant to all antimicrobial classes tested. Success and eradication rates are summarized in Table 16.

Table 16: Clinical Success and Bacteriologic Eradication Rates for Resistant Streptococcus pneumoniae (Community Acquired Pneumonia)
Type of Resistance | Clinical Success | Bacteriologic Eradication
Resistant to 2 antibacterials | 17/18 (94.4%) | 17/18 (94.4%)
Resistant to 3 antibacterials | 14/15 (93.3%) | 14/15 (93.3%)
Resistant to 4 antibacterials | 7/7 (100%) | 7/7 (100%)
Resistant to 5 antibacterials | 0 | 0
Bacteremia with MDRSP | 8/9 (89%) | 8/9 (89%)

14.3 Community-Acquired Pneumonia: 5-Day Treatment Regimen

To evaluate the safety and efficacy of the higher dose and shorter course of LEVAQUIN®, 528 outpatient and hospitalized adults with clinically and radiologically determined mild to severe community-acquired pneumonia were evaluated in a double-blind, randomized, prospective, multicenter study comparing LEVAQUIN® 750 mg, IV or orally, every day for five days or LEVAQUIN® 500 mg IV or orally, every day for 10 days.

Clinical success rates (cure plus improvement) in the clinically evaluable population were 90.9% in the LEVAQUIN® 750 mg group and 91.1% in the LEVAQUIN® 500 mg group. The 95% CI for the difference of response rates (LEVAQUIN® 750 minus LEVAQUIN® 500) was [-5.9, 5.4]. In the clinically evaluable population (31–38 days after enrollment) pneumonia was observed in 7 out of 151 patients in the LEVAQUIN® 750 mg group and 2 out of 147 patients in the LEVAQUIN® 500 mg group. Given the small numbers observed, the significance of this finding cannot be determined statistically. The microbiological efficacy of the 5-day regimen was documented for infections listed in Table 17.

Table 17: Microbiological Eradication Rates (Community-Acquired Pneumonia)
Penicillin susceptible S. pneumoniae | 19/20
Haemophilus influenzae | 12/12
Haemophilus parainfluenzae | 10/10
Mycoplasma pneumoniae | 26/27
Chlamydophila pneumoniae | 13/15

14.4 Acute Bacterial Sinusitis: 5-day and 10–14 day Treatment Regimens

LEVAQUIN® is approved for the treatment of acute bacterial sinusitis (ABS) using either 750 mg by mouth × 5 days or 500 mg by mouth once daily × 10–14 days. To evaluate the safety and efficacy of a high dose short course of LEVAQUIN®, 780 outpatient adults with clinically and radiologically determined acute bacterial sinusitis were evaluated in a double-blind, randomized, prospective, multicenter study comparing LEVAQUIN® 750 mg by mouth once daily for five days to LEVAQUIN® 500 mg by mouth once daily for 10 days.

Clinical success rates (defined as complete or partial resolution of the pre-treatment signs and symptoms of ABS to such an extent that no further antibiotic treatment was deemed necessary) in the microbiologically evaluable population were 91.4% (139/152) in the LEVAQUIN® 750 mg group and 88.6% (132/149) in the LEVAQUIN® 500 mg group at the test-of-cure (TOC) visit (95% CI [-4.2, 10.0] for LEVAQUIN® 750 mg minus LEVAQUIN® 500 mg).

Rates of clinical success by pathogen in the microbiologically evaluable population who had specimens obtained by antral tap at study entry showed comparable results for the five- and ten-day regimens at the test-of-cure visit 22 days post treatment.

Table 18: Clinical Success Rate by Pathogen at the TOC in Microbiologically Evaluable Subjects Who Underwent Antral Puncture (Acute Bacterial Sinusitis)
Pathogen | LEVAQUIN® 750 mg × 5 days | LEVAQUIN® 500 mg × 10 days
Streptococcus pneumoniae [Note: Forty percent of the subjects in this trial had specimens obtained by sinus endoscopy. The efficacy data for subjects whose specimen was obtained endoscopically were comparable to those presented in the above table.] | 25/27 (92.6%) | 26/27 (96.3%)
Haemophilus influenzae | 19/21 (90.5%) | 25/27 (92.6%)
Moraxella catarrhalis | 10/11 (90.9%) | 13/13 (100%)

14.5 Complicated Skin and Skin Structure Infections

Three hundred ninety-nine patients were enrolled in an open-label, randomized, comparative study for complicated skin and skin structure infections. The patients were randomized to receive either LEVAQUIN® 750 mg once daily (IV followed by oral), or an approved comparator for a median of 10 ± 4.7 days. As is expected in complicated skin and skin structure infections, surgical procedures were performed in the LEVAQUIN® and comparator groups. Surgery (incision and drainage or debridement) was performed on 45% of the LEVAQUIN®-treated patients and 44% of the comparator-treated patients, either shortly before or during antibiotic treatment and formed an integral part of therapy for this indication.

Among those who could be evaluated clinically 2–5 days after completion of study drug, overall success rates (improved or cured) were 116/138 (84.1%) for patients treated with LEVAQUIN® and 106/132 (80.3%) for patients treated with the comparator.

Success rates varied with the type of diagnosis ranging from 68% in patients with infected ulcers to 90% in patients with infected wounds and abscesses. These rates were equivalent to those seen with comparator drugs.

14.6 Chronic Bacterial Prostatitis

Adult patients with a clinical diagnosis of prostatitis and microbiological culture results from urine sample collected after prostatic massage (VB3) or expressed prostatic secretion (EPS) specimens obtained via the Meares-Stamey procedure were enrolled in a multicenter, randomized, double-blind study comparing oral LEVAQUIN® 500 mg, once daily for a total of 28 days to oral ciprofloxacin 500 mg, twice daily for a total of 28 days. The primary efficacy endpoint was microbiologic efficacy in microbiologically evaluable patients. A total of 136 and 125 microbiologically evaluable patients were enrolled in the LEVAQUIN® and ciprofloxacin groups, respectively. The microbiologic eradication rate by patient infection at 5–18 days after completion of therapy was 75.0% in the LEVAQUIN® group and 76.8% in the ciprofloxacin group (95% CI [-12.58, 8.98] for LEVAQUIN® minus ciprofloxacin). The overall eradication rates for pathogens of interest are presented in Table 19.

Table 19: Microbiological Eradication Rates (Chronic Bacterial Prostatitis)
 | LEVAQUIN® (N=136) |  | Ciprofloxacin (N=125)
Pathogen | N | Eradication | N | Eradication
E. coli | 15 | 14 (93.3%) | 11 | 9 (81.8%)
E. faecalis | 54 | 39 (72.2%) | 44 | 33 (75.0%)
S. epidermidis [Eradication rates shown are for patients who had a sole pathogen only; mixed cultures were excluded.] | 11 | 9 (81.8%) | 14 | 11 (78.6%)

Eradication rates for S. epidermidis when found with other co-pathogens are consistent with rates seen in pure isolates.

Clinical success (cure + improvement with no need for further antibiotic therapy) rates in microbiologically evaluable population 5–18 days after completion of therapy were 75.0% for LEVAQUIN®-treated patients and 72.8% for ciprofloxacin-treated patients (95% CI [-8.87, 13.27] for LEVAQUIN® minus ciprofloxacin). Clinical long-term success (24–45 days after completion of therapy) rates were 66.7% for the LEVAQUIN®-treated patients and 76.9% for the ciprofloxacin-treated patients (95% CI [-23.40, 2.89] for LEVAQUIN® minus ciprofloxacin).

14.7 Complicated Urinary Tract Infections and Acute Pyelonephritis: 5-day Treatment Regimen

To evaluate the safety and efficacy of the higher dose and shorter course of LEVAQUIN®, 1109 patients with cUTI and AP were enrolled in a randomized, double-blind, multicenter clinical trial conducted in the US from November 2004 to April 2006 comparing LEVAQUIN® 750 mg IV or orally once daily for 5 days (546 patients) with ciprofloxacin 400 mg IV or 500 mg orally twice daily for 10 days (563 patients). Patients with AP complicated by underlying renal diseases or conditions such as complete obstruction, surgery, transplantation, concurrent infection or congenital malformation were excluded. Efficacy was measured by bacteriologic eradication of the baseline organism(s) at the post-therapy visit in patients with a pathogen identified at baseline. The post-therapy (test-of-cure) visit occurred 10 to 14 days after the last active dose of LEVAQUIN® and 5 to 9 days after the last dose of active ciprofloxacin.

The bacteriologic cure rates overall for LEVAQUIN® and control at the test-of-cure (TOC) visit for the group of all patients with a documented pathogen at baseline (modified intent to treat or mITT) and the group of patients in the mITT population who closely followed the protocol (Microbiologically Evaluable) are summarized in Table 20.

Table 20: Bacteriologic Eradication at Test-of-Cure
 | LEVAQUIN® 750 mg orally or IV once daily for 5 days |  | Ciprofloxacin 400 mg IV/500 mg orally twice daily for 10 days |  | Overall Difference [95% CI]
 | n/N | % | n/N | % | LEVAQUIN®-Ciprofloxacin
mITT Population [The mITT population included patients who received study medication and who had a positive (≥10^5 CFU/mL) urine culture with no more than 2 uropathogens at baseline. Patients with missing response were counted as failures in this analysis.]
Overall (cUTI or AP) | 252/333 | 75.7 | 239/318 | 75.2 | 0.5 (-6.1, 7.1)
cUTI | 168/230 | 73.0 | 157/213 | 73.7
AP | 84/103 | 81.6 | 82/105 | 78.1
Microbiologically Evaluable Population [The Microbiologically Evaluable population included patients with a confirmed diagnosis of cUTI or AP, a causative organism(s) at baseline present at ≥ 10^5 CFU/mL, a valid test-of-cure urine culture, no pathogen isolated from blood resistant to study drug, no premature discontinuation or loss to follow-up, and compliance with treatment (among other criteria).]
Overall (cUTI or AP) | 228/265 | 86.0 | 215/241 | 89.2 | -3.2 [-8.9, 2.5]
cUTI | 154/185 | 83.2 | 144/165 | 87.3
AP | 74/80 | 92.5 | 71/76 | 93.4

Microbiologic eradication rates in the Microbiologically Evaluable population at TOC for individual pathogens recovered from patients randomized to LEVAQUIN® treatment are presented in Table 21.

Table 21: Microbiological Eradication Rates for Individual Pathogens Recovered From Patients Randomized to LEVAQUIN® 750 mg QD for 5 Days Treatment
Pathogen | Microbiologic Eradication Rate (n/N) | %
Escherichia coli [The predominant organism isolated from patients with AP was E. coli: 91% (63/69) eradication in AP and 89% (92/103) in patients with cUTI.] | 155/172 | 90
Klebsiella pneumoniae | 20/23 | 87
Proteus mirabilis | 12/12 | 100

14.8 Complicated Urinary Tract Infections and Acute Pyelonephritis: 10-day Treatment Regimen

To evaluate the safety and efficacy of the 250 mg dose, 10 day regimen of LEVAQUIN®, 567 patients with uncomplicated UTI, mild-to-moderate cUTI, and mild-to-moderate AP were enrolled in a randomized, double-blind, multicenter clinical trial conducted in the US from June 1993 to January 1995 comparing LEVAQUIN® 250 mg orally once daily for 10 days (285 patients) with ciprofloxacin 500 mg orally twice daily for 10 days (282 patients). Patients with a resistant pathogen, recurrent UTI, women over age 55 years, and with an indwelling catheter were initially excluded, prior to protocol amendment which took place after 30% of enrollment. Microbiological efficacy was measured by bacteriologic eradication of the baseline organism(s) at 1–12 days post-therapy in patients with a pathogen identified at baseline.

The bacteriologic cure rates overall for LEVAQUIN® and control at the test-of-cure (TOC) visit for the group of all patients with a documented pathogen at baseline (modified intent to treat or mITT) and the group of patients in the mITT population who closely followed the protocol (Microbiologically Evaluable) are summarized in Table 22.

Table 22: Bacteriologic Eradication Overall (cUTI or AP) at Test-Of-Cure [1–9 days posttherapy for 30% of subjects enrolled prior to a protocol amendment; 5–12 days posttherapy for 70% of subjects.]
 | LEVAQUIN® 250 mg once daily for 10 days |  | Ciprofloxacin 500 mg twice daily for 10 days
 | n/N | % | n/N | %
mITT Population [The mITT population included patients who had a pathogen isolated at baseline. Patients with missing response were counted as failures in this analysis.] | 174/209 | 83.3 | 184/219 | 84.0
Microbiologically Evaluable Population [The Microbiologically Evaluable population included mITT patients who met protocol-specified evaluability criteria.] | 164/177 | 92.7 | 159/171 | 93.0

14.9 Inhalational Anthrax (Post-Exposure)

The effectiveness of LEVAQUIN® for this indication is based on plasma concentrations achieved in humans, a surrogate endpoint reasonably likely to predict clinical benefit. LEVAQUIN® has not been tested in humans for the post-exposure prevention of inhalation anthrax. The mean plasma concentrations of LEVAQUIN® associated with a statistically significant improvement in survival over placebo in the rhesus monkey model of inhalational anthrax are reached or exceeded in adult and pediatric patients receiving the recommended oral and intravenous dosage regimens [see Indications and Usage (1.13); Dosage and Administration (2.1, 2.2)].

Levofloxacin pharmacokinetics have been evaluated in adult and pediatric patients. The mean (± SD) steady state peak plasma concentration in human adults receiving 500 mg orally or intravenously once daily is 5.7 ± 1.4 and 6.4 ± 0.8 mcg/mL, respectively; and the corresponding total plasma exposure (AUC0–24) is 47.5 ± 6.7 and 54.6 ± 11.1 mcg.h/mL, respectively. The predicted steady-state pharmacokinetic parameters in pediatric patients ranging in age from 6 months to 17 years receiving 8 mg/kg orally every 12 hours (not to exceed 250 mg per dose) were calculated to be comparable to those observed in adults receiving 500 mg orally once daily [see Clinical Pharmacology (12.3)].

In adults, the safety of LEVAQUIN® for treatment durations of up to 28 days is well characterized. However, information pertaining to extended use at 500 mg daily up to 60 days is limited. Prolonged LEVAQUIN® therapy in adults should only be used when the benefit outweighs the risk.

In pediatric patients, the safety of levofloxacin for treatment durations of more than 14 days has not been studied. An increased incidence of musculoskeletal adverse events (arthralgia, arthritis, tendinopathy, gait abnormality) compared to controls has been observed in clinical studies with treatment duration of up to 14 days. Long-term safety data, including effects on cartilage, following the administration of levofloxacin to pediatric patients is limited [see Warnings and Precautions (5.10), Use in Specific Populations (8.4)].

A placebo-controlled animal study in rhesus monkeys exposed to an inhaled mean dose of 49 LD50 (~2.7 × 10^6) spores (range 17 – 118 LD50) of B. anthracis (Ames strain) was conducted. The minimal inhibitory concentration (MIC) of levofloxacin for the anthrax strain used in this study was 0.125 mcg/mL. In the animals studied, mean plasma concentrations of levofloxacin achieved at expected Tmax (1 hour post-dose) following oral dosing to steady state ranged from 2.79 to 4.87 mcg/mL. Steady state trough concentrations at 24 hours post-dose ranged from 0.107 to 0.164 mcg/mL. Mean (SD) steady state AUC0–24 was 33.4 ± 3.2 mcg.h/mL (range 30.4 to 36.0 mcg.h/mL). Mortality due to anthrax for animals that received a 30 day regimen of oral LEVAQUIN® beginning 24 hrs post exposure was significantly lower (1/10), compared to the placebo group (9/10) [P=0.0011, 2-sided Fisher's Exact Test]. The one levofloxacin treated animal that died of anthrax did so following the 30-day drug administration period.

15 REFERENCES

1. Clinical and Laboratory Standards Institute. Methods for Dilution Antimicrobial Susceptibility Tests for Bacteria That Grow Aerobically. Approved Standard – Eighth Edition. Clinical and Laboratory Standards Institute document M7-A8, Vol. 29, No. 2, CLSI, Wayne, PA, January 2009.
2. Clinical and Laboratory Standards Institute. Performance Standards for Antimicrobial Disk Susceptibility Tests. Approved Standard – Tenth Edition. Clinical and Laboratory Standards Institute document M2-A10, Vol. 29, No. 1, CLSI, Wayne, PA, January 2009.

16 HOW SUPPLIED/STORAGE AND HANDLING

16.1 LEVAQUIN® Tablets

LEVAQUIN® Tablets are supplied as 250, 500, and 750 mg capsule-shaped, coated tablets. LEVAQUIN® Tablets are packaged in bottles and in unit-dose blister strips in the following configurations:

- 500 mg tablets are peach and are imprinted: "LEVAQUIN" on one side and "500" on the other side
  - bottles of 5 (NDC 67296-0372-3)
  - bottles of 7(NDC 67296-0372-2)
  - bottles of 10(NDC 67296-0372-1)

LEVAQUIN® Tablets should be stored at 15° to 30°C (59° to 86°F) in well-closed containers.

LEVAQUIN® Tablets are manufactured for PriCara, Division of Ortho-McNeil-Janssen Pharmaceuticals, Inc., Raritan, NJ 08869 by Janssen Ortho LLC, Gurabo, Puerto Rico 00778.

16.2 LEVAQUIN® Oral Solution

LEVAQUIN® Oral Solution is supplied in a 16 oz. multi-use bottle (NDC 50458-170-01). Each bottle contains 480 mL of the 25 mg/mL levofloxacin oral solution.

LEVAQUIN® Oral Solution should be stored at 25°C (77°F); excursions permitted to 15° – 30°C (59° to 86°F) [refer to USP controlled room temperature].

LEVAQUIN® Oral Solution is manufactured for PriCara, Division of Ortho-McNeil-Janssen Pharmaceuticals, Inc., Raritan, NJ 08869 by Janssen Pharmaceutica N.V., Beerse, Belgium.

16.3 LEVAQUIN® Injection, Single-Use Vials

LEVAQUIN® Injection is supplied in single-use vials. Each vial contains a concentrated solution with the equivalent of 500 mg of levofloxacin in 20 mL vials and 750 mg of levofloxacin in 30 mL vials.

- 25 mg/mL, 20 mL vials (NDC 50458-164-20)
- 25 mg/mL, 30 mL vials (NDC 50458-165-30)

LEVAQUIN® Injection in Single-Use Vials should be stored at controlled room temperature and protected from light.

LEVAQUIN® Injection in Single-Use Vials is manufactured for Ortho-McNeil, Division of Ortho-McNeil-Janssen Pharmaceuticals, Inc., Raritan, NJ 08869 by Janssen Pharmaceutica N.V., Beerse, Belgium.

16.4 LEVAQUIN® Injection Pre-Mixed Solution, Single-Use in Flexible Container

LEVAQUIN® (levofloxacin in 5% dextrose) Injection is supplied as a single-use, premixed solution in flexible containers. Each bag contains a dilute solution with the equivalent of 250, 500, or 750 mg of levofloxacin, respectively, in 5% Dextrose (D5W).

- 5 mg/mL (250 mg), 100 mL flexible container, 50 mL fill (NDC 50458-167-01)
- 5 mg/mL (500 mg), 100 mL flexible container, 100 mL fill (NDC 50458-168-01)
- 5 mg/mL (750 mg), 150 mL flexible container, 150 mL fill (NDC 50458-166-01)

LEVAQUIN® Injection Premix in Flexible Containers should be stored at or below 25°C (77°F); however, brief exposure up to 40°C (104°F) does not adversely affect the product. Avoid excessive heat and protect from freezing and light. LEVAQUIN® Injection Premix in Flexible Containers is manufactured for Ortho-McNeil, Division of Ortho-McNeil-Janssen Pharmaceuticals, Inc., Raritan, NJ 08869 by Hospira, Inc., Austin, TX 78728.

17 PATIENT COUNSELING INFORMATION

See FDA-Approved Medication Guide (17.5)

17.1 Antibacterial Resistance

Antibacterial drugs including LEVAQUIN® should only be used to treat bacterial infections. They do not treat viral infections (e.g., the common cold). When LEVAQUIN® is prescribed to treat a bacterial infection, patients should be told that although it is common to feel better early in the course of therapy, the medication should be taken exactly as directed. Skipping doses or not completing the full course of therapy may (1) decrease the effectiveness of the immediate treatment and (2) increase the likelihood that bacteria will develop resistance and will not be treatable by LEVAQUIN® or other antibacterial drugs in the future.

17.2 Administration with Food, Fluids, and Concomitant Medications

Patients should be informed that LEVAQUIN® Tablets may be taken with or without food. LEVAQUIN® Oral Solution should be taken 1 hour before or 2 hours after eating. The tablet and oral solution should be taken at the same time each day.

Patients should drink fluids liberally while taking LEVAQUIN® to avoid formation of a highly concentrated urine and crystal formation in the urine.

Antacids containing magnesium, or aluminum, as well as sucralfate, metal cations such as iron, and multivitamin preparations with zinc or didanosine should be taken at least two hours before or two hours after oral LEVAQUIN® administration.

17.3 Serious and Potentially Serious Adverse Reactions

Patients should be informed of the following serious adverse reactions that have been associated with LEVAQUIN® or other fluoroquinolone use:

- Tendon Disorders: Patients should contact their healthcare provider if they experience pain, swelling, or inflammation of a tendon, or weakness or inability to use one of their joints; rest and refrain from exercise; and discontinue LEVAQUIN® treatment. The risk of severe tendon disorders with fluoroquinolones is higher in older patients usually over 60 years of age, in patients taking corticosteroid drugs, and in patients with kidney, heart or lung transplants.
- Exacerbation of Myasthenia Gravis: Patients should inform their physician of any history of myasthenia gravis. Patients should notify their physician if they experience any symptoms of muscle weakness, including respiratory difficulties.
- Hypersensitivity Reactions: Patients should be informed that LEVAQUIN® can cause hypersensitivity reactions, even following the first dose. Patients should discontinue the drug at the first sign of a skin rash, hives or other skin reactions, a rapid heartbeat, difficulty in swallowing or breathing, any swelling suggesting angioedema (e.g., swelling of the lips, tongue, face, tightness of the throat, hoarseness), or other symptoms of an allergic reaction.
- Hepatotoxicity: Severe hepatotoxicity (including acute hepatitis and fatal events) has been reported in patients taking LEVAQUIN®. Patients should inform their physician and be instructed to discontinue LEVAQUIN® treatment immediately if they experience any signs or symptoms of liver injury including: loss of appetite, nausea, vomiting, fever, weakness, tiredness, right upper quadrant tenderness, itching, yellowing of the skin and eyes, light colored bowel movements or dark colored urine.
- Convulsions: Convulsions have been reported in patients taking fluoroquinolones, including LEVAQUIN®. Patients should notify their physician before taking this drug if they have a history of convulsions.
- Neurologic Adverse Effects (e.g., dizziness, lightheadedness): Patients should know how they react to LEVAQUIN® before they operate an automobile or machinery or engage in other activities requiring mental alertness and coordination.
- Diarrhea: Diarrhea is a common problem caused by antibiotics which usually ends when the antibiotic is discontinued. Sometimes after starting treatment with antibiotics, patients can develop watery and bloody stools (with or without stomach cramps and fever) even as late as two or more months after having taken the last dose of the antibiotic. If this occurs, patients should contact their physician as soon as possible.
- Peripheral Neuropathies: If symptoms of peripheral neuropathy including pain, burning, tingling, numbness, and/or weakness develop, patients should discontinue treatment and contact their physician.
- Prolongation of the QT Interval: Patients should inform their physician of any personal or family history of QT prolongation or proarrhythmic conditions such as hypokalemia, bradycardia, or recent myocardial ischemia; if they are taking any Class IA (quinidine, procainamide), or Class III (amiodarone, sotalol) antiarrhythmic agents. Patients should notify their physicians if they have any symptoms of prolongation of the QT interval, including prolonged heart palpitations or a loss of consciousness.
- Musculoskeletal Disorders in Pediatric Patients: Parents should inform their child's physician if their child has a history of joint-related problems before taking this drug. Parents of pediatric patients should also notify their child's physician of any tendon or joint-related problems that occur during or following LEVAQUIN® therapy [see Warnings and Precautions (5.10) and Use in Specific Populations (8.4)].
- Photosensitivity/Phototoxicity: Patients should be advised that photosensitivity/phototoxicity has been reported in patients receiving fluoroquinolone antibiotics. Patients should minimize or avoid exposure to natural or artificial sunlight (tanning beds or UVA/B treatment) while taking fluoroquinolones. If patients need to be outdoors when taking fluoroquinolones, they should wear loose-fitting clothes that protect skin from sun exposure and discuss other sun protection measures with their physician. If a sunburn like reaction or skin eruption occurs, patients should contact their physician.

17.4 Drug Interactions with Insulin, Oral Hypoglycemic Agents, and Warfarin

Patients should be informed that if they are diabetic and are being treated with insulin or an oral hypoglycemic agent and a hypoglycemic reaction occurs, they should discontinue LEVAQUIN® and consult a physician.

Patients should be informed that concurrent administration of warfarin and LEVAQUIN® has been associated with increases of the International Normalized Ratio (INR) or prothrombin time and clinical episodes of bleeding. Patients should notify their physician if they are taking warfarin, be monitored for evidence of bleeding, and also have their anticoagulation tests closely monitored while taking warfarin concomitantly.

Manufactured by:

- Janssen Ortho LLC, Gurabo, Puerto Rico 00778 (for the Tablets).
- Janssen Pharmaceutica N.V., Beerse, Belgium (for the Oral Solution and Injection, Single-Use Vials).
- Hospira, Inc., Austin, TX 78728 (for the Injection Pre-Mixed Solution Single-Use in Flexible Container).

Manufactured for:

- PriCara, Division of Ortho-McNeil-Janssen Pharmaceuticals, Inc., Raritan, NJ 08869 (for the Tablets and Oral Solution)
- Ortho-McNeil, Division of Ortho-McNeil-Janssen Pharmaceuticals, Inc., Raritan, NJ 08869 (for the Injection, Single-Use Vials and Injection Pre-Mixed Solution Single-Use in Flexible Container)

©Ortho-McNeil-Janssen Pharmaceuticals, Inc.

Issued June 2011

MEDICATION GUIDE
LEVAQUIN® [Leave ah kwin]
(levofloxacin)
250 mg Tablets, 500 mg Tablets, and 750 mg Tablets
And
LEVAQUIN® (levofloxacin) Oral Solution, 25 mg/mL
And
LEVAQUIN® (levofloxacin) Injection, for Intravenous Use
And
LEVAQUIN® (levofloxacin in 5% dextrose) Injection, for Intravenous Use

Read the Medication Guide that comes with LEVAQUIN® before you start taking it and each time you get a refill. There may be new information. This Medication Guide does not take the place of talking to your healthcare provider about your medical condition or your treatment.

What is the most important information I should know about LEVAQUIN®?

LEVAQUIN® belongs to a class of antibiotics called fluoroquinolones. LEVAQUIN® can cause side effects that may be serious or even cause death. If you get any of the following serious side effects, get medical help right away. Talk with your healthcare provider about whether you should continue to take LEVAQUIN®.

- Tendon rupture or swelling of the tendon (tendinitis).
  - Tendons are tough cords of tissue that connect muscles to bones.
  - Pain, swelling, tears, and inflammation of tendons including the back of the ankle (Achilles), shoulder, hand, or other tendon sites can happen in people of all ages who take fluoroquinolone antibiotics, including LEVAQUIN®. The risk of getting tendon problems is higher if you:
    - are over 60 years of age
    - are taking steroids (corticosteroids)
    - have had a kidney, heart or lung transplant.
  - Swelling of the tendon (tendinitis) and tendon rupture (breakage) have also happened in patients who take fluoroquinolones who do not have the above risk factors.
  - Other reasons for tendon ruptures can include:
    - physical activity or exercise
    - kidney failure
    - tendon problems in the past, such as in people with rheumatoid arthritis (RA).
  - Call your healthcare provider right away at the first sign of tendon pain, swelling or inflammation. Stop taking LEVAQUIN® until tendinitis or tendon rupture has been ruled out by your healthcare provider. Avoid exercise and using the affected area. The most common area of pain and swelling is the Achilles tendon at the back of your ankle. This can also happen with other tendons. Talk to your healthcare provider about the risk of tendon rupture with continued use of LEVAQUIN®. You may need a different antibiotic that is not a fluoroquinolone to treat your infection.
  - Tendon rupture can happen while you are taking or after you have finished taking LEVAQUIN®. Tendon ruptures have happened up to several months after patients have finished taking their fluoroquinolone.
  - Get medical help right away if you get any of the following signs or symptoms of a tendon rupture:
    - hear or feel a snap or pop in a tendon area
    - bruising right after an injury in a tendon area
    - unable to move the affected area or bear weight
- Worsening of myasthenia gravis (a disease that causes muscle weakness). Fluoroquinolones like LEVAQUIN® may cause worsening of myasthenia gravis symptoms, including muscle weakness and breathing problems. Call your healthcare provider right away if you have any worsening muscle weakness or breathing problems.

See the section "What are the possible side effects of LEVAQUIN®?" for more information about side effects.

What is LEVAQUIN®?

LEVAQUIN® is a fluoroquinolone antibiotic medicine used in adults, 18 years or older, to treat certain infections caused by certain germs called bacteria.

Children have a higher chance of getting bone, joint, or tendon (musculoskeletal) problems such as pain or swelling while taking LEVAQUIN®.

In children 6 months and older who have breathed the anthrax bacteria germ:

- LEVAQUIN® is used to prevent anthrax disease (inhalation anthrax).
- It is not known if it is safe to use LEVAQUIN® in children for more than 14 days.

It is not known if LEVAQUIN® is safe and works in children under the age of 6 months.

Sometimes infections are caused by viruses rather than by bacteria. Examples include viral infections in the sinuses and lungs, such as the common cold or flu. Antibiotics, including LEVAQUIN®, do not kill viruses.

Call your healthcare provider if you think your condition is not getting better while you are taking LEVAQUIN®.

Who should not take LEVAQUIN®?

Do not take LEVAQUIN® if you have ever had a severe allergic reaction to an antibiotic known as a fluoroquinolone, or if you are allergic to any of the ingredients in LEVAQUIN®. Ask your healthcare provider if you are not sure. See the list of the ingredients in LEVAQUIN® at the end of this Medication Guide.

What should I tell my healthcare provider before taking LEVAQUIN®?

See "What is the most important information I should know about LEVAQUIN®?"

Tell your healthcare provider about all your medical conditions, including if you:

- have tendon problems
- have a disease that causes muscle weakness (myasthenia gravis)
- have central nervous system problems (such as epilepsy)
- have nerve problems
- have or anyone in your family has an irregular heartbeat, especially a condition called "QT prolongation."
- have low blood potassium (hypokalemia)
- have a history of seizures
- have bone and joint problems
- have kidney problems. You may need a lower dose of LEVAQUIN® if your kidneys do not work well.
- have liver problems
- have rheumatoid arthritis (RA) or other history of joint problems
- are pregnant or planning to become pregnant. It is not known if LEVAQUIN® will harm your unborn child.
- are breast-feeding or planning to breast-feed. LEVAQUIN® is thought to pass into breast milk. You and your healthcare provider should decide whether you will take LEVAQUIN® or breast-feed.

Tell your healthcare provider about all the medicines you take, including prescription and non-prescription medicines, vitamins, herbal and dietary supplements. LEVAQUIN® and other medicines can affect each other causing side effects. Especially tell your healthcare provider if you take:

- an NSAID (Non-Steroidal Anti-Inflammatory Drug). Many common medicines for pain relief are NSAIDs. Taking an NSAID while you take LEVAQUIN® or other fluoroquinolones may increase your risk of central nervous system effects and seizures. See "What are the possible side effects of LEVAQUIN®?"
- an oral anti-diabetes medicine or insulin
- a blood thinner (warfarin, Coumadin, Jantoven)
- a medicine to control your heart rate or rhythm (antiarrhythmics). See "What are the possible side effects of LEVAQUIN®?".
- an anti-psychotic medicine
- a tricyclic antidepressant
- a water pill (diuretic)
- a steroid medicine. Corticosteroids taken by mouth or by injection may increase the chance of tendon injury. See "What is the most important information I should know about LEVAQUIN®?".
- theophylline (Theo-24®, Elixophyllin®, Theochron®, Uniphyl®, Theolair®)
- Certain medicines may keep LEVAQUIN® from working correctly. Take LEVAQUIN® Tablets or Oral Solution either 2 hours before or 2 hours after taking these products:
  - an antacid, multivitamin, or other product that has magnesium, aluminum, iron, or zinc.
  - sucralfate (Carafate®)
  - didanosine (Videx®,Videx® EC)

Ask your healthcare provider if you are not sure if any of your medicines are listed above.

Know the medicines you take. Keep a list of your medicines and show it to your healthcare provider and pharmacist when you get a new medicine.

How should I take LEVAQUIN®?

- Take LEVAQUIN® exactly as prescribed by your healthcare provider.
- Take LEVAQUIN® at about the same time each day.
- Drink plenty of fluids while taking LEVAQUIN®.
- LEVAQUIN® Tablets can be taken with or without food.
- Take LEVAQUIN® Oral Solution 1 hour before or 2 hours after eating.
- If you miss a dose of LEVAQUIN®, take it as soon as you remember. Do not take more than one dose in one day.
- LEVAQUIN® for Injection is given to you by intravenous (I.V.) infusion into your vein, slowly, over 60 or 90 minutes, as prescribed by your healthcare provider. See "What are the possible side effects of LEVAQUIN®?"
- Do not skip any doses, or stop taking LEVAQUIN® even if you begin to feel better, until you finish your prescribed treatment, unless:
  - you have tendon effects (see "What is the most important information I should know about LEVAQUIN®?"),
  - you have a serious allergic reaction (see "What are the possible side effects of LEVAQUIN®?"), or
  - your healthcare provider tells you to stop.
- This will help make sure that all of the bacteria are killed and lower the chance that the bacteria will become resistant to LEVAQUIN®. If this happens, LEVAQUIN® and other antibiotic medicines may not work in the future.

If you take too much, call your healthcare provider or get medical help immediately.

If you have been prescribed LEVAQUIN® after being exposed to anthrax:

- LEVAQUIN® has been approved to lessen the chance of getting anthrax disease or worsening of the disease after you are exposed to the anthrax bacteria germ.
- Take LEVAQUIN® exactly as prescribed by your healthcare provider. Do not stop taking LEVAQUIN® without talking with your healthcare provider. If you stop taking LEVAQUIN® too soon, it may not keep you from getting the anthrax disease.
- Side effects may happen while you are taking LEVAQUIN®. When taking LEVAQUIN® to prevent anthrax infection, you and your healthcare provider should talk about whether the risks of stopping your medicine too soon are more important than the risks of side effects with LEVAQUIN®. It is not known if it is safe to use LEVAQUIN® for more than 28 days in adults and for more than 14 days in children 6 months of age and older.
- If you are pregnant, or plan to become pregnant while taking LEVAQUIN®, you and your healthcare provider should decide whether the benefits of taking LEVAQUIN® for anthrax are more important than the risks.

What should I avoid while taking LEVAQUIN®?

- LEVAQUIN® can make you feel dizzy and lightheaded. Do not drive, operate machinery, or do other activities that require mental alertness or coordination until you know how LEVAQUIN® affects you.

- Avoid sunlamps, tanning beds, and try to limit your time in the sun. LEVAQUIN® can make your skin sensitive to the sun (photosensitivity) and the light from sunlamps and tanning beds. You could get severe sunburn, blisters or swelling of your skin. If you get any of these symptoms while taking LEVAQUIN®, call your healthcare provider right away. You should use a sunscreen and wear a hat and clothes that cover your skin if you have to be in sunlight.

What are the possible side effects of LEVAQUIN®?

LEVAQUIN®can cause side effects that may be serious or even cause death. See "What is the most important information I should know about LEVAQUIN®?"

Other serious side effects of LEVAQUIN® include:

- Liver damage (hepatotoxicity): Liver damage (hepatotoxicity) can happen in people who take LEVAQUIN®. Call your healthcare provider right away if you have unexplained symptoms such as:
  - nausea or vomiting,
  - stomach pain,
  - fever,
  - weakness,
  - abdominal pain or tenderness,
  - itching,
  - unusual tiredness,
  - loss of appetite,
  - light colored bowel movements,
  - dark colored urine or yellowing of your skin or the whites of your eyes.

- Central Nervous System Effects. Seizures have been reported in people who take fluoroquinolone antibiotics including LEVAQUIN®. Tell your healthcare provider if you have a history of seizures. Ask your healthcare provider whether taking LEVAQUIN® will change your risk of having a seizure.
  Central Nervous System (CNS) side effects may happen as soon as after taking the first dose of LEVAQUIN®. Talk to your healthcare provider right away if you get any of these side effects, or other changes in mood or behavior:
  - seizures
  - hear voices, see things, or sense things that are not there (hallucinations)
  - feel restless
  - tremors
  - feel anxious or nervous
  - confusion
  - depression
  - trouble sleeping
  - nightmares
  - feel lightheaded
  - feel more suspicious (paranoia)
  - suicidal thoughts or acts

- Serious allergic reactions.
  Allergic reactions can happen in people taking fluoroquinolones, including LEVAQUIN®, even after only one dose. Stop taking LEVAQUIN® and get emergency medical help right away if you get any of the following symptoms of a severe allergic reaction:
  - hives
  - trouble breathing or swallowing
  - swelling of the lips, tongue, face
  - throat tightness, hoarseness
  - rapid heartbeat
  - faint
  - Yellowing of the skin or eyes. Stop taking LEVAQUIN® and tell your healthcare provider right away if you get yellowing of your skin or white part of your eyes, or if you have dark urine. These can be signs of a serious reaction to LEVAQUIN® (a liver problem).

- Skin rash
  Skin rash may happen in people taking LEVAQUIN®, even after only one dose. Stop taking LEVAQUIN® at the first sign of a skin rash and call your healthcare provider. Skin rash may be a sign of a more serious reaction to LEVAQUIN®.

- Intestine infection (Pseudomembranous colitis)
  Pseudomembranous colitis can happen with most antibiotics, including LEVAQUIN®. Call your healthcare provider right away if you get watery diarrhea, diarrhea that does not go away, or bloody stools. You may have stomach cramps and a fever. Pseudomembranous colitis can happen 2 or more months after you have finished your antibiotic.

- Changes in sensation and possible nerve damage (Peripheral Neuropathy)
  Damage to the nerves in arms, hands, legs, or feet can happen in people taking fluoroquinolones, including LEVAQUIN®. Talk with your healthcare provider right away if you get any of the following symptoms of peripheral neuropathy in your arms, hands, legs, or feet:
  - pain
  - burning
  - tingling
  - numbness
  - weakness

LEVAQUIN® may need to be stopped to prevent permanent nerve damage.

- Serious heart rhythm changes (QT prolongation and torsades de pointes)
  Tell your healthcare provider right away if you have a change in your heart beat (a fast or irregular heartbeat), or if you faint. LEVAQUIN® may cause a rare heart problem known as prolongation of the QT interval. This condition can cause an abnormal heartbeat and can be very dangerous. The chances of this happening are higher in people:
  - who are elderly
  - with a family history of prolonged QT interval
  - with low blood potassium (hypokalemia)
  - who take certain medicines to control heart rhythm (antiarrhythmics)

- Changes in blood sugar [low blood sugar (hypoglycemia) and high blood sugar (hyperglycemia)]
  People who take LEVAQUIN® and other fluoroquinolone medicines with oral anti-diabetes medicines or with insulin can get low blood sugar (hypoglycemia) and high blood sugar (hyperglycemia). Follow your healthcare provider's instructions for how often to check your blood sugar. If you have diabetes and you get low blood sugar while taking LEVAQUIN®, stop taking LEVAQUIN® and call your healthcare provider right away. Your antibiotic medicine may need to be changed.

- Sensitivity to sunlight (photosensitivity)
  See "What should I avoid while taking LEVAQUIN®?"

- Joint Problems
  Increased chance of problems with joints and tissues around joints in children. Tell your child's healthcare provider if your child has any joint problems during or after treatment with LEVAQUIN®.

The most common side effects of LEVAQUIN® include:

- dizziness
- headache
- constipation
- nausea
- diarrhea

In children 6 months and older who take LEVAQUIN® to prevent anthrax disease, vomiting is also common.

Low blood pressure can happen with LEVAQUIN® given by IV injection if it is given too fast. Tell your healthcare provider if you feel dizzy, or faint during a treatment with LEVAQUIN®.

LEVAQUIN® may cause false-positive urine screening results for opiates when testing is done with some commercially available kits. A positive result should be confirmed using a more specific test.

These are not all the possible side effects of LEVAQUIN®. Tell your healthcare provider about any side effect that bothers you or that does not go away.

Call your doctor for medical advice about side effects. You may report side effects to FDA at 1-800-FDA-1088.

How should I store LEVAQUIN®?

Store LEVAQUIN® Film-Coated Tablets at 59° to 86° F (15°C to 30°C). Keep the container closed tightly.

Store LEVAQUIN® Oral Solution at 59° to 86° F (15°C to 30°C).

Keep LEVAQUIN® and all medicines out of the reach of children.

General Information about LEVAQUIN®

Medicines are sometimes prescribed for purposes other than those listed in a Medication Guide. Do not use LEVAQUIN® for a condition for which it is not prescribed. Do not give LEVAQUIN® to other people, even if they have the same symptoms that you have. It may harm them.

This Medication Guide summarizes the most important information about LEVAQUIN®. If you would like more information about LEVAQUIN®, talk with your healthcare provider. You can ask your healthcare provider or pharmacist for information about LEVAQUIN® that is written for healthcare professionals. For more information go to www.levaquin.com or call 1-800-526-7736.

What are the ingredients in LEVAQUIN®?

- 250 mg LEVAQUIN® Film-Coated Tablets:
  - Active ingredient: levofloxacin.
  - Inactive ingredients: hypromellose, crospovidone, microcrystalline cellulose, magnesium stearate, polyethylene glycol, titanium dioxide, polysorbate 80 and synthetic red iron oxide.
- 500 mg LEVAQUIN® Film-Coated Tablets:
  - Active ingredient: levofloxacin.
  - Inactive ingredients: hypromellose, crospovidone, microcrystalline cellulose, magnesium stearate, polyethylene glycol, titanium dioxide, polysorbate 80 and synthetic red and yellow iron oxides.
- 750 mg LEVAQUIN® Film-Coated Tablets:
  - Active ingredient: levofloxacin.
  - Inactive ingredients: hypromellose, crospovidone, microcrystalline cellulose, magnesium stearate, polyethylene glycol, titanium dioxide, polysorbate 80.
- LEVAQUIN® Oral Solution (25 mg/mL):
  - Active ingredient: levofloxacin.
  - Inactive ingredients: sucrose, glycerin, sucralose, hydrochloric acid, purified water, propylene glycol, artificial and natural flavors, benzyl alcohol, ascorbic acid, and caramel color. It may also contain a solution of sodium hydroxide for pH adjustment.
    - LEVAQUIN® Oral Solution may look clear yellow to clear greenish-yellow in color.
- LEVAQUIN® Injection in Single-Use Vials:
  - Active ingredient: levofloxacin.
  - Inactive ingredients: water for injection. LEVAQUIN® for Injection Single Use Vials do not contain any preservatives.
- LEVAQUIN® Injection Premix in Single-Use Flexible Containers:
  - Active ingredient: levofloxacin.
  - Inactive ingredients: Dextrose (D5W). Solutions of hydrochloric acid and sodium hydroxide may have been added to adjust the pH.

Revised June 2011

Manufactured by:
Janssen Ortho LLC, Gurabo, Puerto Rico 00778 (Tablets).
Janssen Pharmaceutica N.V., Beerse, Belgium (Oral Solution, Injection Single-Use Vials).
Hospira, Inc., Austin, TX 78728 (Injection Premix).

Manufactured for:
PriCara, Division of Ortho-McNeil-Janssen Pharmaceuticals, Inc., Raritan, NJ 08869 (Tablets, Oral Solution)
Ortho-McNeil, Division of Ortho-McNeil-Janssen Pharmaceuticals, Inc., Raritan, NJ 08869 (Injection Single-Use Vials, Injection Premix)

©Ortho-McNeil-Janssen Pharmaceuticals, Inc.

This Medication Guide has been approved by the U.S. Food and Drug Administration.

copy of label